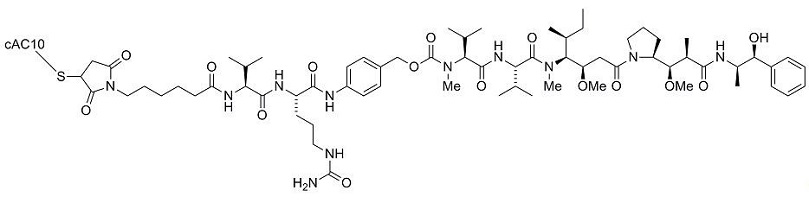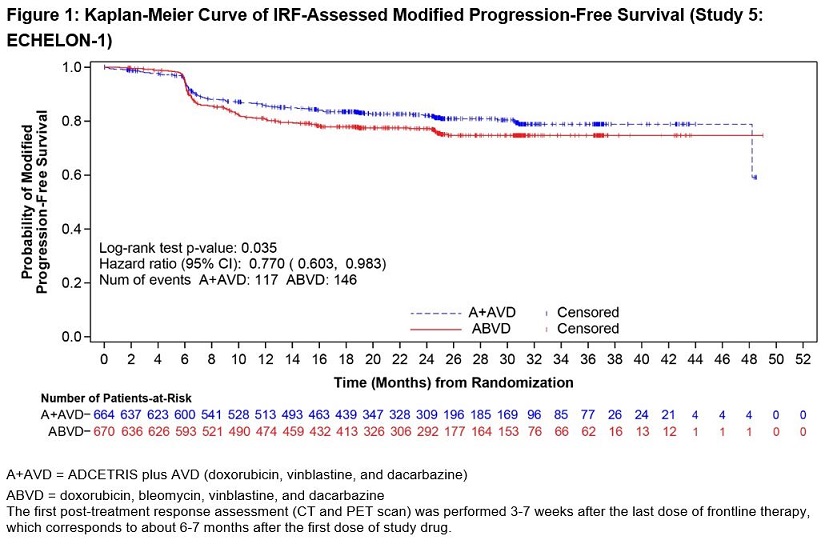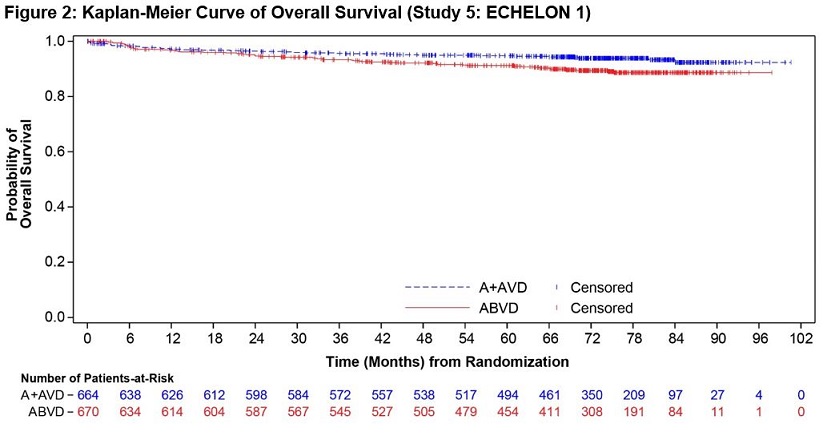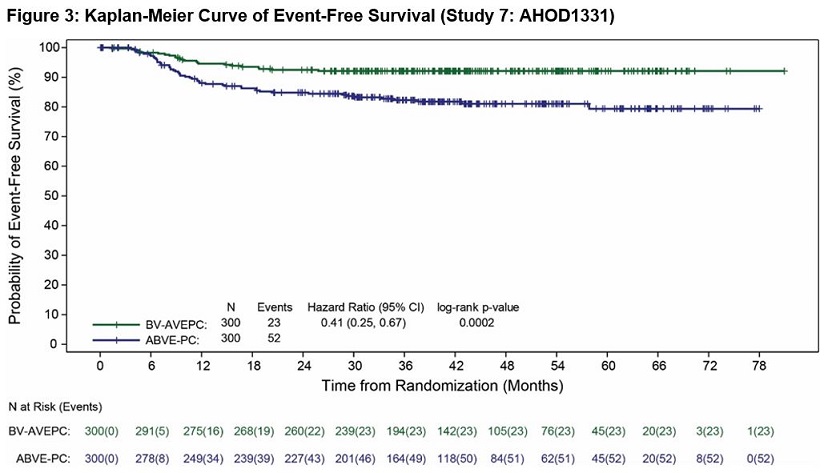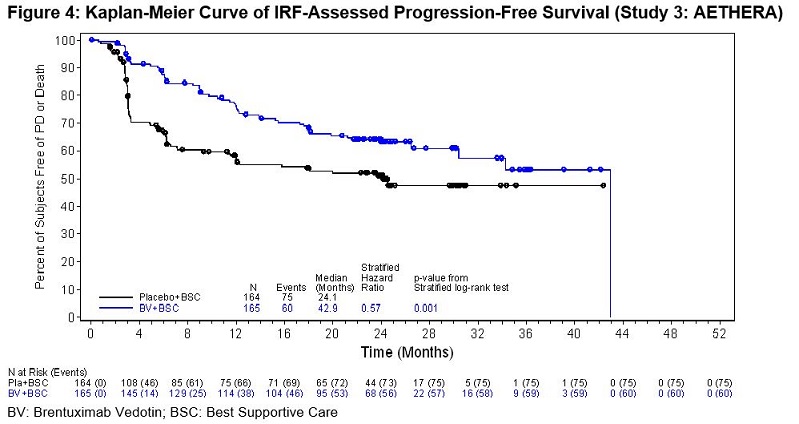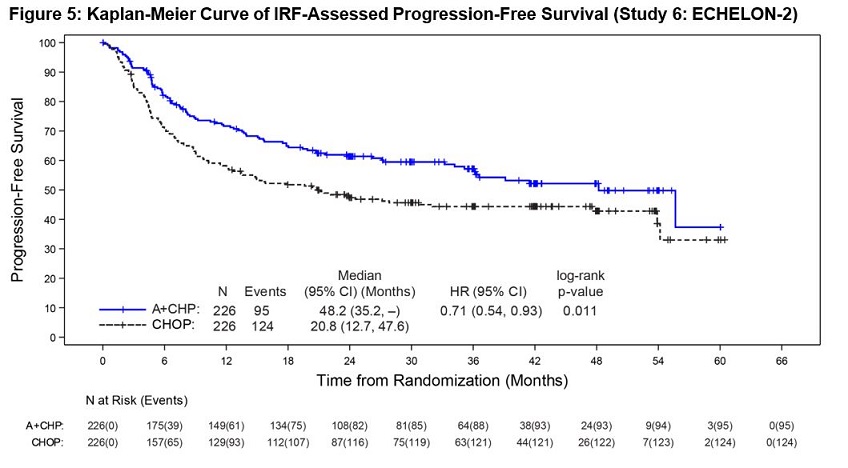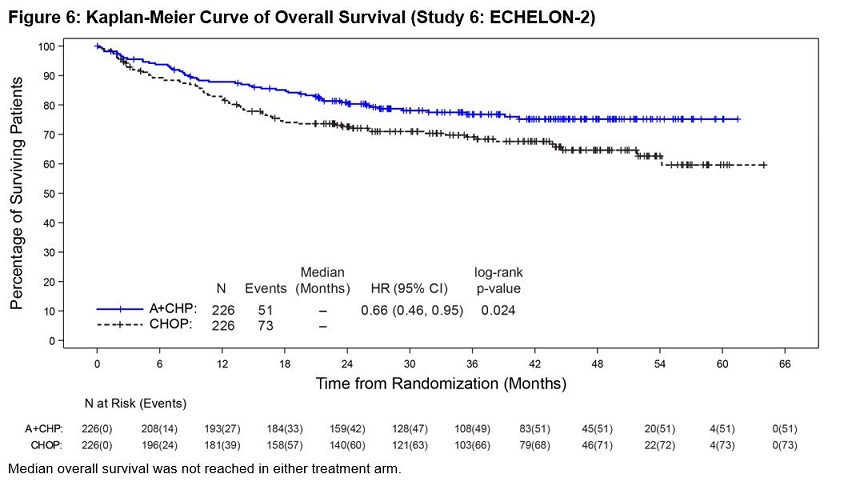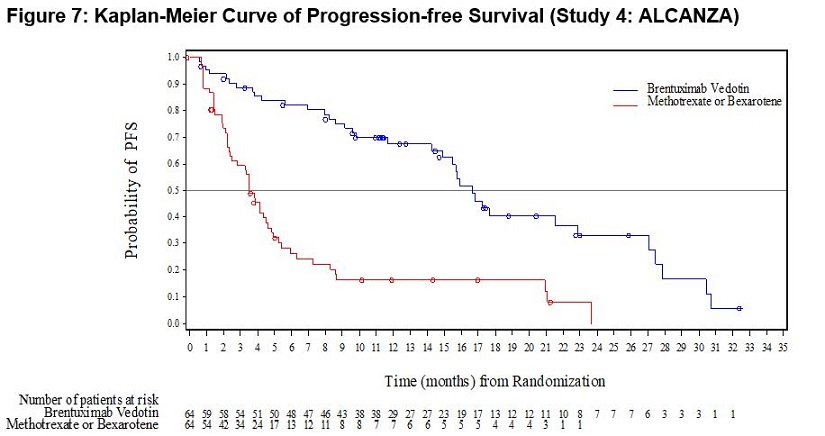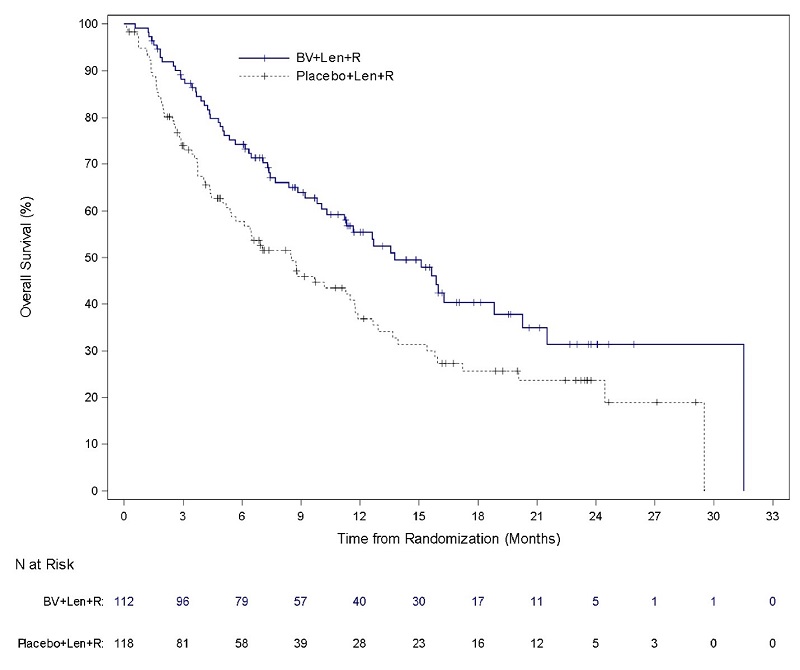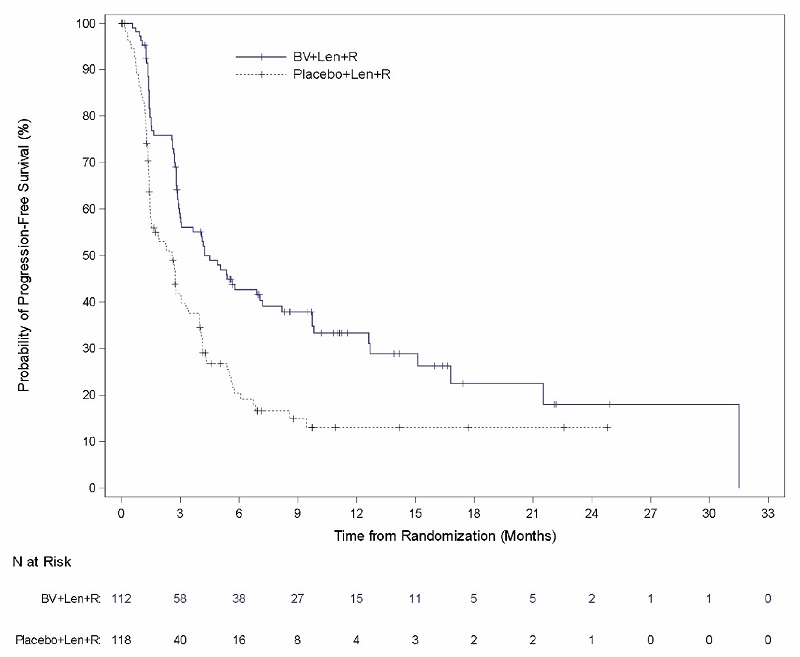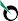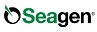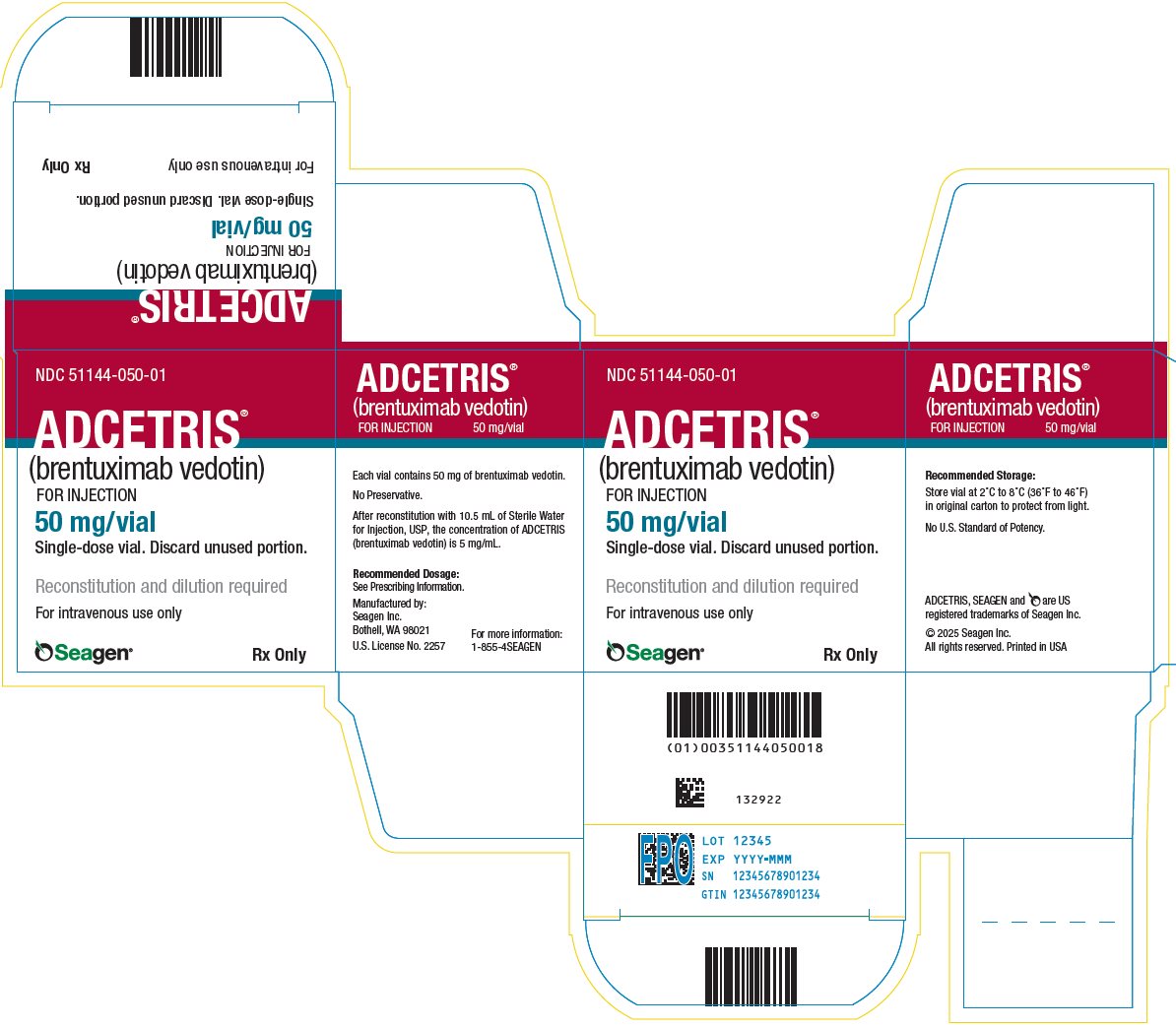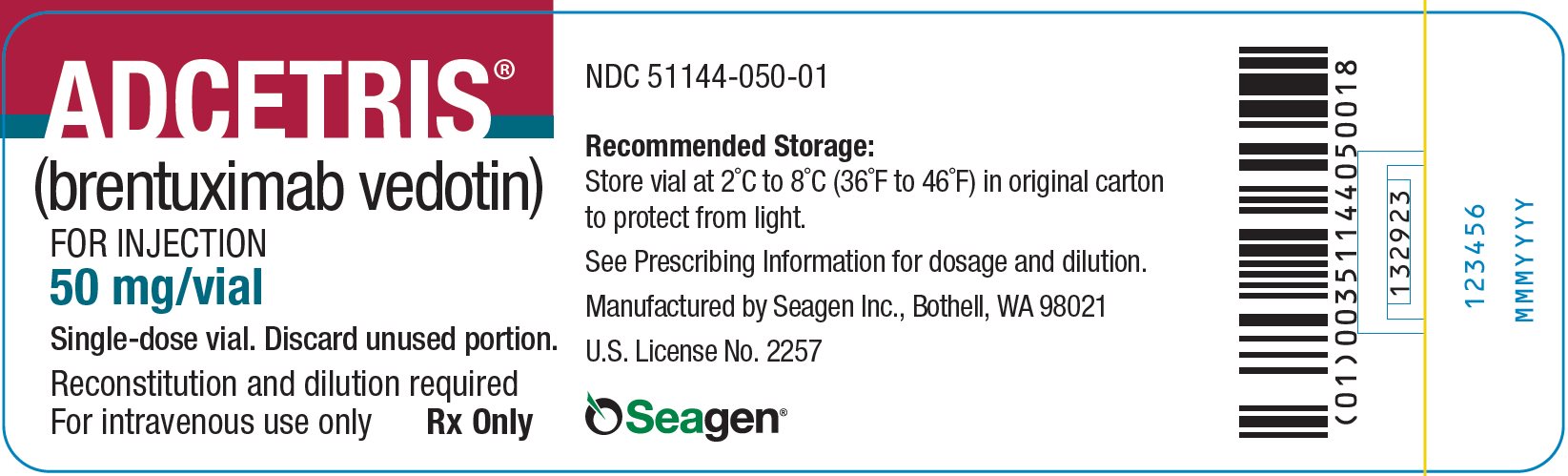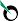 DRUG LABEL: ADCETRIS
NDC: 51144-050 | Form: INJECTION, POWDER, LYOPHILIZED, FOR SOLUTION
Manufacturer: SEAGEN INC.
Category: prescription | Type: HUMAN PRESCRIPTION DRUG LABEL
Date: 20251111

ACTIVE INGREDIENTS: Brentuximab Vedotin 50 mg/10.5 mL
INACTIVE INGREDIENTS: Trehalose Dihydrate; Trisodium Citrate Dihydrate; Citric Acid Monohydrate; Polysorbate 80

HIGHLIGHTS OF PRESCRIBING INFORMATION

These highlights do not include all the information needed to use ADCETRIS safely and effectively. See full prescribing information for ADCETRIS.
ADCETRIS® (brentuximab vedotin) for injection, for intravenous use
Initial U.S. approval: 2011

WARNING: PROGRESSIVE MULTIFOCAL LEUKOENCEPHALOPATHY (PML)

See full prescribing information for complete boxed warning.

JC virus infection resulting in PML and death can occur in patients receiving ADCETRIS (5.9, 6.1).

RECENT MAJOR CHANGES

Indications and Usage (1.8) | 2/2025
Dosage and Administration (2.1, 2.3, 2.4, 2.5) | 2/2025
Warnings and Precautions (5.1) | 2/2025

1 INDICATIONS AND USAGE

ADCETRIS is a CD30-directed antibody and microtubule inhibitor conjugate indicated for treatment of:

- Adult patients with previously untreated Stage III or IV classical Hodgkin lymphoma (cHL), in combination with doxorubicin, vinblastine, and dacarbazine (1.1).
- Pediatric patients 2 years and older with previously untreated high risk classical Hodgkin lymphoma (cHL), in combination with doxorubicin, vincristine, etoposide, prednisone, and cyclophosphamide (1.2).
- Adult patients with classical Hodgkin lymphoma (cHL) at high risk of relapse or progression as post-autologous hematopoietic stem cell transplantation (auto-HSCT) consolidation (1.3).
- Adult patients with classical Hodgkin lymphoma (cHL) after failure of auto-HSCT or after failure of at least two prior multi-agent chemotherapy regimens in patients who are not auto-HSCT candidates (1.4).
- Adult patients with previously untreated systemic anaplastic large cell lymphoma (sALCL) or other CD30-expressing peripheral T-cell lymphomas (PTCL), including angioimmunoblastic T-cell lymphoma and PTCL not otherwise specified (NOS), in combination with cyclophosphamide, doxorubicin, and prednisone (1.5).
- Adult patients with systemic anaplastic large cell lymphoma (sALCL) after failure of at least one prior multi-agent chemotherapy regimen (1.6).
- Adult patients with primary cutaneous anaplastic large cell lymphoma (pcALCL) or CD30-expressing mycosis fungoides (MF) who have received prior systemic therapy (1.7).
- Adult patients with relapsed or refractory large B-cell lymphoma (LBCL), including diffuse large B-cell lymphoma (DLBCL) NOS, DLBCL arising from indolent lymphoma, or high-grade B-cell lymphoma (HGBL), after two or more lines of systemic therapy who are not eligible for auto-HSCT or CAR T-cell therapy, in combination with lenalidomide and a rituximab product (1.8).

2 DOSAGE AND ADMINISTRATION

- Administer only as an intravenous infusion over 30 minutes (2.1).
- The recommended dosage as monotherapy for adult patients is 1.8 mg/kg up to a maximum of 180 mg every 3 weeks (2.1).
- The recommended dosage in combination with chemotherapy for adult patients with previously untreated Stage III or IV cHL is 1.2 mg/kg up to a maximum of 120 mg every 2 weeks for a maximum of 12 doses (2.1).
- The recommended dosage in combination with chemotherapy for pediatric patients 2 years and older with previously untreated high risk cHL is 1.8 mg/kg up to a maximum of 180 mg every 3 weeks for a maximum of 5 doses (2.1).
- The recommended dosage in combination with chemotherapy for adult patients with previously untreated PTCL is 1.8 mg/kg up to a maximum of 180 mg every 3 weeks for 6 to 8 doses (2.1).
- The recommended dosage in combination with lenalidomide and a rituximab product for adult patients with relapsed or refractory LBCL is 1.2 mg/kg up to a maximum of 120 mg every 3 weeks (2.1).
- Avoid use in patients with severe renal impairment (2.2)
- Reduce dose in patients with mild hepatic impairment; avoid use in patients with moderate or severe hepatic impairment (2.3).

3 DOSAGE FORMS AND STRENGTHS

For injection: 50 mg lyophilized powder in a single-dose vial (3).

4 CONTRAINDICATIONS

Concomitant use with bleomycin due to pulmonary toxicity (4).

5 WARNINGS AND PRECAUTIONS

- Peripheral neuropathy: Monitor patients for neuropathy and institute dose modifications accordingly (5.1).
- Anaphylaxis and infusion reactions: If an infusion reaction occurs, interrupt the infusion. If anaphylaxis occurs, immediately discontinue the infusion (5.2).
- Hematologic toxicities: Monitor complete blood counts. Monitor for signs of infection. Manage using dose delays and growth factor support (5.3).
- Serious infections and opportunistic infections: Closely monitor patients for the emergence of bacterial, fungal or viral infections (5.4).
- Tumor lysis syndrome: Closely monitor patients with rapidly proliferating tumor or high tumor burden (5.5).
- Hepatotoxicity: Monitor liver enzymes and bilirubin (5.8).
- Pulmonary toxicity: Monitor patients for new or worsening symptoms (5.10).
- Serious dermatologic reactions: Discontinue if Stevens-Johnson syndrome or toxic epidermal necrolysis occurs (5.11).
- Gastrointestinal complications: Monitor patients for new or worsening symptoms (5.12).
- Hyperglycemia: Monitor patients for new or worsening hyperglycemia. Manage with anti-hyperglycemic medications as clinically indicated (5.13).
- Embryo-Fetal toxicity: Can cause fetal harm. Advise females of reproductive potential and males with female partners of reproductive potential of the potential risk to a fetus and to use effective contraception (5.14, 8.1, 8.3).

6 ADVERSE REACTIONS

The most common adverse reactions (≥20%) are peripheral neuropathy, nausea, fatigue, musculoskeletal pain, constipation, diarrhea, vomiting, pyrexia, upper respiratory tract infection, mucositis, abdominal pain, and rash.

The most common laboratory abnormalities (≥20%) are decreased neutrophils, increased creatinine, decreased hemoglobin, decreased lymphocytes, increased glucose, increased alanine aminotransferase (ALT), and increased aspartate aminotransferase (AST) (6.1).
To report SUSPECTED ADVERSE REACTIONS, contact Seagen Inc. at 1-855-473-2436 or FDA at 1-800-FDA-1088 or www.fda.gov/Safety/MedWatch.

7 DRUG INTERACTIONS

Concomitant use of strong CYP3A4 inhibitors or inducers has the potential to affect the exposure to monomethyl auristatin E (MMAE) (7.1).

8 USE IN SPECIFIC POPULATIONS

- Moderate or severe hepatic impairment or severe renal impairment: MMAE exposure and adverse reactions are increased (6, 7, 8.6, 8.7).
- Lactation: Advise women not to breastfeed (8.2).

FULL PRESCRIBING INFORMATION

WARNING: PROGRESSIVE MULTIFOCAL LEUKOENCEPHALOPATHY (PML)

JC virus infection resulting in PML and death can occur in patients receiving ADCETRIS [see Warnings and Precautions (5.9), Adverse Reactions (6.1)].

1 INDICATIONS AND USAGE

1.1 Previously Untreated Stage III or IV Classical Hodgkin Lymphoma (cHL), in Combination with Chemotherapy

ADCETRIS is indicated for the treatment of adult patients with previously untreated Stage III or IV cHL, in combination with doxorubicin, vinblastine, and dacarbazine.

1.2 Previously Untreated High Risk Classical Hodgkin Lymphoma (cHL), in Combination with Chemotherapy

ADCETRIS is indicated for the treatment of pediatric patients 2 years and older with previously untreated high risk cHL, in combination with doxorubicin, vincristine, etoposide, prednisone, and cyclophosphamide.

1.3 Classical Hodgkin Lymphoma (cHL) Consolidation

ADCETRIS is indicated for the treatment of adult patients with cHL at high risk of relapse or progression as post-autologous hematopoietic stem cell transplantation (auto-HSCT) consolidation.

1.4 Relapsed Classical Hodgkin Lymphoma (cHL)

ADCETRIS is indicated for the treatment of adult patients with cHL after failure of auto-HSCT or after failure of at least two prior multi-agent chemotherapy regimens in patients who are not auto-HSCT candidates.

1.5 Previously Untreated Systemic Anaplastic Large Cell Lymphoma (sALCL) or Other CD30-Expressing Peripheral T-cell Lymphomas (PTCL), in Combination with Chemotherapy

ADCETRIS is indicated for the treatment of adult patients with previously untreated sALCL or other CD30-expressing PTCL, including angioimmunoblastic T-cell lymphoma and PTCL not otherwise specified (NOS), in combination with cyclophosphamide, doxorubicin, and prednisone.

1.6 Relapsed Systemic Anaplastic Large Cell Lymphoma (sALCL)

ADCETRIS is indicated for the treatment of adult patients with sALCL after failure of at least one prior multi-agent chemotherapy regimen.

1.7 Relapsed Primary Cutaneous Anaplastic Large Cell Lymphoma (pcALCL) or CD30-Expressing Mycosis Fungoides (MF)

ADCETRIS is indicated for the treatment of adult patients with pcALCL or CD30-expressing MF who have received prior systemic therapy.

1.8 Relapsed or Refractory Large B-Cell Lymphoma (LBCL)

ADCETRIS in combination with lenalidomide and a rituximab product is indicated for the treatment of adult patients with relapsed or refractory LBCL, including diffuse large B-cell lymphoma (DLBCL) NOS, DLBCL arising from indolent lymphoma, or high-grade B-cell lymphoma (HGBL), after two or more lines of systemic therapy who are not eligible for auto-HSCT or chimeric antigen receptor (CAR) T-cell therapy.

2 DOSAGE AND ADMINISTRATION

2.1 Recommended Dosage

The recommended ADCETRIS dosage is provided in Table 1. Administer ADCETRIS as a 30-minute intravenous infusion.

For recommended dosage for patients with renal or hepatic impairment, see Dosage and Administration (2.2 and 2.3).

For dosing instructions of combination agents administered with ADCETRIS, see Clinical Studies (14.1, 14.2, and 14.5) and the manufacturer’s prescribing information.

Table 1: Recommended ADCETRIS Dosage
Indication | Recommended Dose [The dose for patients weighing greater than 100 kg should be calculated based on a weight of 100 kg.] | Frequency and Duration
Adult patients with previously untreated Stage III or IV classical Hodgkin lymphoma | 1.2 mg/kg up to a maximum of 120 mg in combination with chemotherapy | Administer every 2 weeks until a maximum of 12 doses, disease progression, or unacceptable toxicity
Pediatric patients with previously untreated high risk classical Hodgkin lymphoma | 1.8 mg/kg up to a maximum of 180 mg in combination with chemotherapy | Administer every 3 weeks with each cycle of chemotherapy for a maximum of 5 doses
Adult patients with classical Hodgkin lymphoma consolidation | 1.8 mg/kg up to a maximum of 180 mg | Initiate ADCETRIS treatment within 4‑6 weeks post-auto-HSCT or upon recovery from auto-HSCT Administer every 3 weeks until a maximum of 16 cycles, disease progression, or unacceptable toxicity
Adult patients with relapsed classical Hodgkin lymphoma | 1.8 mg/kg up to a maximum of 180 mg | Administer every 3 weeks until disease progression or unacceptable toxicity
Adult patients with previously untreated systemic ALCL or other CD30-expressing peripheral T-cell lymphomas | 1.8 mg/kg up to a maximum of 180 mg in combination with chemotherapy | Administer every 3 weeks with each cycle of chemotherapy for 6 to 8 doses
Adult patients with relapsed Systemic ALCL | 1.8 mg/kg up to a maximum of 180 mg | Administer every 3 weeks until disease progression or unacceptable toxicity
Adult patients with relapsed primary cutaneous ALCL or CD30-expressing mycosis fungoides | 1.8 mg/kg up to a maximum of 180 mg | Administer every 3 weeks until a maximum of 16 cycles, disease progression, or unacceptable toxicity
Adult patients with relapsed or refractory LBCL | 1.2 mg/kg up to a maximum of 120 mg in combination with lenalidomide and rituximab [Starting with cycle 2, rituximab intravenous treatment could be substituted with rituximab and hyaluronidase human via subcutaneous injection every 3 weeks.] | Administer every 3 weeks until disease progression, or unacceptable toxicity

2.2 Recommended Dosage in Patients with Renal Impairment

No dosage adjustment is required for mild renal impairment (CrCL greater than 50‑80 mL/min) and moderate renal impairment (CrCL 30-50 mL/min).

Avoid use in patients with severe (CrCL less than 30 mL/min) renal impairment [see Warnings and Precautions (5.6)].

2.3 Recommended Dosage in Patients with Hepatic Impairment

Adult patients with previously untreated Stage III or IV classical Hodgkin lymphoma

Reduce the dosage of ADCETRIS to 0.9 mg/kg up to a maximum of 90 mg every 2 weeks for patients with mild hepatic impairment (Child-Pugh A).

Avoid use in patients with moderate (Child-Pugh B) and severe (Child-Pugh C) hepatic impairment [see Warnings and Precautions (5.7)].

Adult patients with relapsed or refractory LBCL

Reduce the dosage of ADCETRIS to 0.9 mg/kg up to a maximum of 90 mg every 3 weeks for patients with mild hepatic impairment (total bilirubin ≤ upper limit of normal [ULN] and aspartate transaminase [AST] > ULN, or total bilirubin >1 to 1.5 × ULN and any AST).

Avoid use in patients with moderate and severe hepatic impairment (total bilirubin >1.5 × ULN) [see Warnings and Precautions (5.7)].

Hepatic impairment is defined per the National Cancer Institute Organ Dysfunction Working Group.

All other indications

Reduce the dosage of ADCETRIS to 1.2 mg/kg up to a maximum of 120 mg every 3 weeks for patients with mild hepatic impairment (Child-Pugh A).

Avoid use in patients with moderate (Child-Pugh B) and severe (Child-Pugh C) hepatic impairment [see Warnings and Precautions (5.7)].

2.4 Recommended Prophylactic Medications

In adult patients with previously untreated Stage III or IV cHL who are treated with ADCETRIS + doxorubicin, vinblastine, and dacarbazine (AVD), administer G‑CSF beginning with Cycle 1.

In pediatric patients with previously untreated high risk cHL who are treated with ADCETRIS + doxorubicin, vincristine, etoposide, prednisone, and cyclophosphamide (AVEPC), administer G-CSF beginning with Cycle 1.

In adult patients with previously untreated PTCL who are treated with ADCETRIS + cyclophosphamide, doxorubicin, and prednisone (CHP), administer G-CSF beginning with Cycle 1.

In adult patients with relapsed or refractory LBCL who are treated with ADCETRIS + lenalidomide + rituximab, administer G-CSF beginning with Cycle 1.

2.5 Dosage Modifications for Adverse Reactions

Table 2: Dosage Modifications for Peripheral Neuropathy or Neutropenia in Adult Patients [see Warnings and Precautions (5.1, 5.3)]
Recommended ADCETRIS Dosage from Table 1 [The dose for patients weighing greater than 100 kg should be calculated based on a weight of 100 kg.] | Monotherapy or Combination Therapy | Severity [Grades based on National Cancer Institute Common Terminology Criteria for Adverse Events (CTCAE) Version 5.] | Dosage Modification
Peripheral Neuropathy
1.2 mg/kg up to a maximum of 120 mg every 2 weeks | In combination with chemotherapy | Grade 2 | Reduce dose to 0.9 mg/kg up to a maximum of 90 mg every 2 weeks.
1.2 mg/kg up to a maximum of 120 mg every 2 weeks | In combination with chemotherapy | Grade 3 | Hold ADCETRIS dosing until improvement to Grade 2 or lower. Restart at 0.9 mg/kg up to a maximum of 90 mg every 2 weeks. Consider modifying the dose of other neurotoxic chemotherapy agents.
1.2 mg/kg up to a maximum of 120 mg every 2 weeks | In combination with chemotherapy | Grade 4 | Discontinue dosing.
1.2 mg/kg up to a maximum of 120 mg every 3 weeks | In combination with lenalidomide and rituximab | Grade 2 | Sensory neuropathy: If resolves to Grade 1 or lower before the next scheduled dose, resume at the same dose level. If Grade 2 persists at the next scheduled dose, reduce one dose level. Motor neuropathy: Reduce dosage to 0.9 mg/kg up to a maximum of 90 mg every 3 weeks.
1.2 mg/kg up to a maximum of 120 mg every 3 weeks | In combination with lenalidomide and rituximab | Grade 3 | Sensory neuropathy: Hold ADCETRIS dosing until improvement to Grade 2 or lower, then restart treatment at a reduced dosage of 0.9 mg/kg up to a maximum of 90 mg every 3 weeks. Motor neuropathy: Discontinue dosing.
1.2 mg/kg up to a maximum of 120 mg every 3 weeks | In combination with lenalidomide and rituximab | Grade 4 | Discontinue dosing.
1.8 mg/kg up to a maximum of 180 mg every 3 weeks | As monotherapy | New or worsening Grade 2 or 3 | Hold dosing until improvement to baseline or Grade 1. Restart at 1.2 mg/kg up to a maximum of 120 mg every 3 weeks.
1.8 mg/kg up to a maximum of 180 mg every 3 weeks | As monotherapy | Grade 4 | Discontinue dosing.
1.8 mg/kg up to a maximum of 180 mg every 3 weeks | In combination with chemotherapy | Grade 2 | Sensory neuropathy: Continue treatment at same dose. Motor neuropathy: Reduce dose to 1.2 mg/kg up to a maximum of 120 mg every 3 weeks.
1.8 mg/kg up to a maximum of 180 mg every 3 weeks | In combination with chemotherapy | Grade 3 | Sensory neuropathy: Reduce dose to 1.2 mg/kg, up to a maximum of 120 mg every 3 weeks. Motor neuropathy: Discontinue dosing.
1.8 mg/kg up to a maximum of 180 mg every 3 weeks | In combination with chemotherapy | Grade 4 | Discontinue dosing.
Neutropenia
1.2 mg/kg up to a maximum of 120 mg every 2 weeks | In combination with chemotherapy | Grade 3 or 4 | Administer G‑CSF prophylaxis for subsequent cycles for patients not receiving primary G‑CSF prophylaxis.
1.2 mg/kg up to a maximum of 120 mg every 3 weeks | In combination with lenalidomide and rituximab | Grade 3 or 4 | Hold dosing until improvement to baseline or Grade 2 or lower. Reduce/discontinue lenalidomide dose per prescribing information. Administer G-CSF prophylaxis for subsequent cycles for patients not receiving primary G-CSF prophylaxis.
1.8 mg/kg up to a maximum of 180 mg every 3 weeks | In combination with chemotherapy | Grade 3 or 4 | Administer G-CSF prophylaxis in subsequent cycles for patients not receiving primary G-CSF prophylaxis.
1.8 mg/kg up to a maximum of 180 mg every 3 weeks | As monotherapy | Grade 3 or 4 | Hold dosing until improvement to baseline or Grade 2 or lower. Consider G-CSF prophylaxis for subsequent cycles.
1.8 mg/kg up to a maximum of 180 mg every 3 weeks | As monotherapy | Recurrent Grade 4 despite G‑CSF prophylaxis | Consider discontinuation or dose reduction to 1.2 mg/kg up to a maximum of 120 mg every 3 weeks.

Table 3: Dosage Modifications for Peripheral Neuropathy or Neutropenia in Pediatric Patients
Recommended ADCETRIS Dosage from Table 1 [The dose for patients weighing greater than 100 kg should be calculated based on a weight of 100 kg.] | Severity | Dosage Modification
Peripheral Neuropathy [Peripheral neuropathy was assessed using the Balis scale.]
1.8 mg/kg up to a maximum of 180 mg every 3 weeks | Grade 2 | Reduce dose of vincristine per prescribing information. Continue dosing with ADCETRIS. If neuropathy improves to Grade ≤1 by day 8 of next cycle, then resume vincristine at full dose.
1.8 mg/kg up to a maximum of 180 mg every 3 weeks | Grade 3 | Discontinue vincristine. First Occurrence: Hold ADCETRIS dosing until improvement to ≤ Grade 2 then restart at 1.2 mg/kg up to a maximum of 120 mg. Second Occurrence: Hold until improvement to ≤ Grade 2 then restart at 0.8 mg/kg up to a maximum of 80 mg. Third Occurrence: Discontinue ADCETRIS.
1.8 mg/kg up to a maximum of 180 mg every 3 weeks | Grade 4 | Discontinue ADCETRIS and vincristine.
Neutropenia
1.8 mg/kg up to a maximum of 180 mg every 3 weeks | Grade 3 or 4 | Reduce dose to 1.2 mg/kg up to a maximum of 120 mg every 3 weeks in patients who are unable to start a cycle >5 weeks after the start of the previous cycle (>2-week delay) due to neutropenia.

2.6 Instructions for Preparation and Administration

Administration

- Administer ADCETRIS as an intravenous infusion only.
- Do not mix ADCETRIS with, or administer as an infusion with, other medicinal products.

Reconstitution

- Follow procedures for proper handling and disposal of hazardous drugs^1.
- Use appropriate aseptic technique for reconstitution and preparation of dosing solutions.
- Determine the number of 50 mg vials needed based on the patient’s weight and the prescribed dose [see Dosage and Administration (2.1)].
- Reconstitute each 50 mg vial of ADCETRIS with 10.5 mL of Sterile Water for Injection to yield a single-dose solution containing 5 mg/mL brentuximab vedotin.
- Direct the stream toward the wall of vial and not directly at the cake or powder.
- Gently swirl the vial to aid dissolution. DO NOT SHAKE.
- Parenteral drug products should be inspected visually for particulate matter and discoloration prior to administration, whenever solution and container permit. The reconstituted solution should be clear to slightly opalescent, colorless, and free of visible particulates.
- Following reconstitution, dilute immediately into an infusion bag. If not diluted immediately, store the solution refrigerated at 2°C to 8°C (36°F to 46°F) and use within 24 hours of reconstitution. DO NOT FREEZE.
- Discard any unused portion left in the vial.

Dilution

- Calculate the required volume of 5 mg/mL reconstituted ADCETRIS solution needed.
- Withdraw this amount from the vial and immediately add it to an infusion bag containing 0.9% Sodium Chloride Injection, USP, 5% Dextrose Injection or Lactated Ringer's Injection to achieve a final concentration of 0.4 mg/mL to 1.8 mg/mL brentuximab vedotin.
- Gently invert the bag to mix the solution.
- Following dilution, infuse the ADCETRIS solution immediately. If not used immediately, store the solution refrigerated at 2°C to 8°C (36°F to 46°F) and use within 24 hours of reconstitution. DO NOT FREEZE.

3 DOSAGE FORMS AND STRENGTHS

For injection: 50 mg of brentuximab vedotin as a sterile, white to off-white lyophilized, preservative-free cake or powder in a single-dose vial for reconstitution.

4 CONTRAINDICATIONS

ADCETRIS is contraindicated with concomitant bleomycin due to pulmonary toxicity (e.g., interstitial infiltration and/or inflammation) [see Adverse Reactions (6.1)].

5 WARNINGS AND PRECAUTIONS

5.1 Peripheral Neuropathy

ADCETRIS treatment causes a peripheral neuropathy that is predominantly sensory. Cases of peripheral motor neuropathy have also been reported. ADCETRIS-induced peripheral neuropathy is cumulative.

In studies of ADCETRIS as monotherapy, 62% of patients experienced any grade of peripheral neuropathy. The median time to onset was 3 months (range, 0–12). Of the patients who experienced neuropathy, 62% had complete resolution, 24% had partial improvement, and 14% had no improvement at their last evaluation. The median time from onset to resolution or improvement was 5 months (range, 0–45). Of the patients with ongoing neuropathy (38%), 71% had Grade 1, 24% had Grade 2, and 4% had Grade 3.

In ECHELON-1 (Study 5), 67% of patients treated with ADCETRIS + AVD experienced any grade of peripheral neuropathy. The median time to onset of any grade was 2 months (range, 0–7), of Grade 2 was 3 months (range, 0–6) and of Grade 3 was 4 months (range, <1–7). By the time of the primary analysis, 43% of affected patients had complete resolution, 24% had partial improvement, and 33% had no improvement at their last evaluation. The median time from onset to resolution or improvement of any grade was 2 months (range, 0–32).

At the updated analysis of ECHELON-1, 72% of the patients who experienced peripheral neuropathy had complete resolution, 14% had partial improvement, and 14% had no improvement. The median time to partial improvement was 2.9 months (range, <1–50), and the median time to complete resolution was 6.6 months (range, <1–67). Of the patients with ongoing neuropathy (28%), 57% had Grade 1, 30% had Grade 2, 12% had Grade 3, and <1% had Grade 4.

In ECHELON-2 (Study 6), 52% of patients treated with ADCETRIS + CHP experienced new or worsening peripheral neuropathy of any grade (by maximum grade, 34% Grade 1, 15% Grade 2, 3% Grade 3, <1% Grade 4). The peripheral neuropathy was predominantly sensory (94% sensory, 16% motor) and had a median onset time of 2 months (range, <1–5). At last evaluation, 50% had complete resolution of neuropathy, 12% had partial improvement, and 38% had no improvement. The median time to resolution or improvement overall was 4 months (range, 0–45). Of patients with ongoing neuropathy (50%), 72% had Grade 1, 25% had Grade 2, and 3% had Grade 3.

In AHOD1331 (Study 7), 20% of pediatric patients treated with ADCETRIS + AVEPC experienced peripheral neuropathy of any grade (7% Grade 3, <1% Grade 4). Peripheral neuropathy was predominantly sensory. Of the patients who experienced peripheral neuropathy, 81% experienced sensory neuropathy and 29% experienced motor neuropathy.

In ECHELON-3 (Study 8), 27% of patients treated with ADCETRIS + lenalidomide + a rituximab product experienced peripheral neuropathy of any grade (by maximum grade, 14% Grade 1, 7% Grade 2, 5% Grade 3). The peripheral neuropathy was predominantly sensory and had a median onset time of 3 months (range, <1-10). Peripheral neuropathy resulted in ADCETRIS dose reduction in 6% of treated patients, and permanent discontinuation in 4.5%. At last evaluation, 7% of the patients who experienced peripheral neuropathy had complete resolution of neuropathy, 10% had partial improvement, and 83% had no improvement. The median time to resolution was 2 months (range <1-3). The median time to improvement was 4 months (range, 3-4). Of patients who experienced peripheral neuropathy, 93% had ongoing peripheral neuropathy (47% had Grade 1, 33% had Grade 2, and 13% had Grade 3).

Monitor patients for symptoms of neuropathy, such as hypoesthesia, hyperesthesia, paresthesia, discomfort, a burning sensation, neuropathic pain, or weakness. Patients experiencing new or worsening peripheral neuropathy may require a delay, change in dose, or discontinuation of ADCETRIS [see Dosage and Administration (2.3) and Adverse Reactions (6.1)].

5.2 Anaphylaxis and Infusion Reactions

Infusion-related reactions, including anaphylaxis, have occurred with ADCETRIS. Monitor patients during infusion. If anaphylaxis occurs, immediately and permanently discontinue administration of ADCETRIS and administer appropriate medical therapy. If an infusion-related reaction occurs, interrupt the infusion and institute appropriate medical management. Patients who have experienced a prior infusion-related reaction should be premedicated for subsequent infusions. Premedication may include acetaminophen, an antihistamine, and a corticosteroid.

5.3 Hematologic Toxicities

Fatal and serious cases of febrile neutropenia have been reported with ADCETRIS. Prolonged (≥1 week) severe neutropenia and Grade 3 or Grade 4 thrombocytopenia or anemia can occur with ADCETRIS.

Start primary prophylaxis with G‑CSF beginning with Cycle 1 for adult patients who receive ADCETRIS in combination for previously untreated Stage III or IV cHL or previously untreated PTCL or relapsed or refractory LBCL, and pediatric patients who receive ADCETRIS in combination with chemotherapy for previously untreated high risk cHL [see Dosage and Administration (2.3) and Adverse Reactions (6.1)].

Monitor complete blood counts prior to each dose of ADCETRIS. Monitor more frequently for patients with Grade 3 or 4 neutropenia. Monitor patients for fever. If Grade 3 or 4 neutropenia develops, consider dose delays, reductions, discontinuation, or G-CSF prophylaxis with subsequent ADCETRIS doses [see Dosage and Administration (2.2, 2.3)].

5.4 Serious Infections and Opportunistic Infections

Serious infections and opportunistic infections such as pneumonia, bacteremia, and sepsis or septic shock (including fatal outcomes) have been reported in patients treated with ADCETRIS. Monitor patients closely during treatment for the emergence of possible bacterial, fungal, or viral infections.

5.5 Tumor Lysis Syndrome

Patients with rapidly proliferating tumor and high tumor burden may be at increased risk of tumor lysis syndrome. Monitor closely and take appropriate measures.

5.6 Increased Toxicity in the Presence of Severe Renal Impairment

The frequency of ≥ Grade 3 adverse reactions and deaths was greater in patients with severe renal impairment compared to patients with normal renal function. Due to higher MMAE exposure, ≥Grade 3 adverse reactions may be more frequent in patients with severe renal impairment compared to patients with normal renal function. Avoid the use of ADCETRIS in patients with severe renal impairment [creatinine clearance (CrCL) <30 mL/min] [see Use in Specific Populations (8.6)].

5.7 Increased Toxicity in the Presence of Moderate or Severe Hepatic Impairment

The frequency of ≥ Grade 3 adverse reactions and deaths was greater in patients with moderate and severe hepatic impairment compared to patients with normal hepatic function. Avoid the use of ADCETRIS in patients with moderate (Child-Pugh B) or severe (Child-Pugh C) hepatic impairment [see Use in Specific Populations (8.7)].

5.8 Hepatotoxicity

Fatal and serious cases of hepatotoxicity have occurred in patients receiving ADCETRIS. Cases were consistent with hepatocellular injury, including elevations of transaminases and/or bilirubin. Cases have occurred after the first dose of ADCETRIS or after ADCETRIS rechallenge. Preexisting liver disease, elevated baseline liver enzymes, and concomitant medications may also increase the risk. Monitor liver enzymes and bilirubin. Patients experiencing new, worsening, or recurrent hepatotoxicity may require a delay, change in dose, or discontinuation of ADCETRIS.

5.9 Progressive Multifocal Leukoencephalopathy

Fatal cases of JC virus infection resulting in PML have been reported in ADCETRIS-treated patients. First onset of symptoms occurred at various times from initiation of ADCETRIS therapy, with some cases occurring within 3 months of initial exposure. In addition to ADCETRIS therapy, other possible contributory factors include prior therapies and underlying disease that may cause immunosuppression. Consider the diagnosis of PML in any patient presenting with new-onset signs and symptoms of central nervous system abnormalities. Hold ADCETRIS dosing for any suspected case of PML and discontinue ADCETRIS dosing if a diagnosis of PML is confirmed.

5.10 Pulmonary Toxicity

Fatal and serious events of noninfectious pulmonary toxicity including pneumonitis, interstitial lung disease, and acute respiratory distress syndrome (ARDS), have been reported. Monitor patients for signs and symptoms of pulmonary toxicity, including cough and dyspnea. In the event of new or worsening pulmonary symptoms, hold ADCETRIS dosing during evaluation and until symptomatic improvement.

5.11 Serious Dermatologic Reactions

Fatal and serious cases of Stevens-Johnson syndrome (SJS) and toxic epidermal necrolysis (TEN) have been reported with ADCETRIS. If SJS or TEN occurs, discontinue ADCETRIS and administer appropriate medical therapy.

5.12 Gastrointestinal Complications

Fatal and serious events of acute pancreatitis have been reported. Other fatal and serious gastrointestinal (GI) complications include perforation, hemorrhage, erosion, ulcer, intestinal obstruction, enterocolitis, neutropenic colitis, and ileus. Lymphoma with preexisting GI involvement may increase the risk of perforation. In the event of new or worsening GI symptoms, including severe abdominal pain, perform a prompt diagnostic evaluation and treat appropriately.

5.13 Hyperglycemia

Serious events of hyperglycemia, such as new-onset hyperglycemia, exacerbation of pre-existing diabetes mellitus, and ketoacidosis (including fatal outcomes) have been reported in ADCETRIS-treated patients. In studies of ADCETRIS monotherapy, 8% of patients experienced any grade hyperglycemia, with 6% experiencing Grade 3 or 4 hyperglycemia. The median time to onset for any grade or Grade 3 or 4 was 1 month (range, 0-10). Hyperglycemia occurred more frequently in patients with high body mass index or diabetes. Monitor serum glucose and if hyperglycemia develops, administer anti-hyperglycemic medications as clinically indicated.

5.14 Embryo-Fetal Toxicity

Based on the mechanism of action and findings in animals, ADCETRIS can cause fetal harm when administered to a pregnant woman. There are no adequate and well-controlled studies of ADCETRIS in pregnant women. In animal reproduction studies, brentuximab vedotin caused embryo-fetal toxicities, including significantly decreased embryo viability, and fetal malformations at maternal exposures that were similar to the clinical dose of 1.8 mg/kg every three weeks.

Advise females of reproductive potential to use effective contraception during ADCETRIS treatment and for 2 months after the last dose of ADCETRIS. Advise male patients with female partners of reproductive potential to use effective contraception during ADCETRIS treatment and for 4 months after the last dose of ADCETRIS. Advise a pregnant woman of the potential risk to the fetus [see Use in Specific Populations (8.1, 8.3)].

6 ADVERSE REACTIONS

The following clinically significant adverse reactions are described elsewhere in the labeling:

- Peripheral Neuropathy [see Warnings and Precautions (5.1)]
- Anaphylaxis and Infusion Reactions [see Warnings and Precautions (5.2)]
- Hematologic Toxicities [see Warnings and Precautions (5.3)]
- Serious Infections and Opportunistic Infections [see Warnings and Precautions (5.4)]
- Tumor Lysis Syndrome [see Warnings and Precautions (5.5)]
  - Increased Toxicity in the Presence of Severe Renal Impairment [see Warnings and Precautions (5.6)]
- Increased Toxicity in the Presence of Moderate or Severe Hepatic Impairment [see Warnings and Precautions (5.7)]
- Hepatotoxicity [see Warnings and Precautions (5.8)]
- Progressive Multifocal Leukoencephalopathy [see Warnings and Precautions (5.9)]
- Pulmonary Toxicity [see Warnings and Precautions (5.10)]
- Serious Dermatologic Reactions [see Warnings and Precautions (5.11)]
- Gastrointestinal Complications [see Warnings and Precautions (5.12)]
- Hyperglycemia [see Warnings and Precautions (5.13)]

6.1 Clinical Trials Experience

Because clinical trials are conducted under widely varying conditions, adverse reaction rates observed in clinical trials of a drug cannot be directly compared to rates in the clinical trials of another drug and may not reflect the rates observed in practice.

The data below reflect exposure to ADCETRIS in 931 adult patients with cHL including 662 patients who received ADCETRIS in combination with chemotherapy in a randomized controlled trial, 269 who received ADCETRIS as monotherapy (167 in a randomized controlled trial and 102 in a single arm trial), and 296 pediatric patients with high risk cHL who received ADCETRIS in combination with chemotherapy. Data summarizing ADCETRIS exposure are also provided for 347 patients with T-cell lymphoma, including 223 patients with PTCL who received ADCETRIS in combination with chemotherapy in a randomized, double-blind, controlled trial; 58 patients with sALCL who received ADCETRIS monotherapy in a single-arm trial; and 66 patients with pcALCL or CD30-expressing MF who received ADCETRIS monotherapy in a randomized, controlled trial. ADCETRIS was administered intravenously at a dose of either 1.2 mg/kg every 2 weeks in combination with AVD, 1.8 mg/kg every 3 weeks in combination with AVEPC in pediatric patients, 1.8 mg/kg every 3 weeks in combination with CHP, or 1.8 mg/kg every 3 weeks as monotherapy.

The most common adverse reactions (≥20%) with monotherapy in adult patients were peripheral neuropathy, fatigue, upper respiratory tract infection, musculoskeletal pain, nausea, diarrhea, pyrexia, rash, and cough.

The most common laboratory abnormalities (≥20%) with monotherapy in adult patients were decreased neutrophils, increased creatinine, increased glucose, increased aspartate aminotransferase (AST), increased alanine aminotransferase (ALT), decreased lymphocytes, decreased hemoglobin, and decreased platelets.

The most common adverse reactions (≥20%) with combination therapy in adult patients were peripheral neuropathy, nausea, fatigue, musculoskeletal pain, constipation, diarrhea, mucositis, vomiting, abdominal pain, pyrexia, alopecia, upper respiratory tract infection, and rash.

The most common laboratory abnormalities (≥20%) with combination therapy in adult patients were decreased neutrophils, increased creatinine, decreased hemoglobin, decreased lymphocytes, increased ALT, increased AST, increased glucose, and increased uric acid.

The most common Grade ≥3 adverse reactions (≥5%) in combination with AVEPC in pediatric patients were neutropenia, anemia, thrombocytopenia, febrile neutropenia, stomatitis, and infection.

Previously Untreated Stage III or IV Classical Hodgkin Lymphoma (Study 5: ECHELON-1)

ADCETRIS in combination with AVD was evaluated for the treatment of previously untreated patients with Stage III or IV cHL in a randomized, open-label, multicenter clinical trial of 1334 patients. Patients were randomized to receive up to 6 cycles of ADCETRIS + AVD or ABVD on Days 1 and 15 of each 28‑day cycle. The recommended starting dose of ADCETRIS was 1.2 mg/kg intravenously over 30 minutes, administered approximately 1 hour after completion of AVD therapy. A total of 1321 patients received at least one dose of study treatment (662 ADCETRIS + AVD, 659 ABVD). The median number of treatment cycles in each study arm was 6 (range, 1–6); 76% of patients on the ADCETRIS + AVD arm received 12 doses of ADCETRIS [see Clinical Studies (14.1)].

After 75% of patients had started study treatment, the use of prophylactic G‑CSF was recommended with the initiation of treatment for all ADCETRIS + AVD treated patients, based on the observed rates of neutropenia and febrile neutropenia [see Dosage and Administration (2.2)]. Among 579 patients on the ADCETRIS + AVD arm who did not receive G‑CSF primary prophylaxis beginning with Cycle 1, 96% experienced neutropenia (21% with Grade 3; 67% with Grade 4), and 21% had febrile neutropenia (14% with Grade 3; 6% with Grade 4). Among 83 patients on the ADCETRIS + AVD arm who received G-CSF primary prophylaxis beginning with Cycle 1, 61% experienced neutropenia (13% with Grade 3; 27% with Grade 4), and 11% experienced febrile neutropenia (8% with Grade 3; 2% with Grade 4).

Serious adverse reactions were reported in 43% of ADCETRIS + AVD-treated patients and 27% of ABVD-treated patients. The most common serious adverse reactions in ADCETRIS + AVD-treated patients were febrile neutropenia (17%), pyrexia (7%), neutropenia and pneumonia (3% each).

Adverse reactions that led to dose delays of one or more drugs in more than 5% of ADCETRIS + AVD-treated patients were neutropenia (21%) and febrile neutropenia (8%) [see Dosage and Administration (2.2)]. Adverse reactions led to treatment discontinuation of one or more drugs in 13% of ADCETRIS + AVD-treated patients. Seven percent of patients treated with ADCETRIS + AVD discontinued due to peripheral neuropathy.

There were 9 on-study deaths among ADCETRIS + AVD-treated patients; 7 were associated with neutropenia, and none of these patients had received G-CSF prior to developing neutropenia.

Table 4: Adverse Reactions Reported in ≥10% of ADCETRIS + AVD-Treated Patients in Previously Untreated Stage III or IV Classical Hodgkin Lymphoma (Study 5: ECHELON‑1)
 | ADCETRIS + AVD Total N = 662 % of patients |  |  | ABVD Total N = 659 % of patients
Body System Adverse Reaction | Any Grade | Grade 3 | Grade 4 | Any Grade | Grade 3 | Grade 4
Blood and lymphatic system disorders
Anemia [Derived from laboratory values and adverse reaction data; data are included for clinical relevance irrespective of rate between arms] | 98 | 11 | <1 | 92 | 6 | <1
Neutropenia | 91 | 20 | 62 | 89 | 31 | 42
Febrile neutropenia | 19 | 13 | 6 | 8 | 6 | 2
Gastrointestinal disorders
Constipation | 42 | 2 | - | 37 | <1 | <1
Vomiting | 33 | 3 | - | 28 | 1 | -
Diarrhea | 27 | 3 | <1 | 18 | <1 | -
Stomatitis | 21 | 2 | - | 16 | <1 | -
Abdominal pain | 21 | 3 | - | 10 | <1 | -
Nervous system disorders
Peripheral sensory neuropathy | 65 | 10 | <1 | 41 | 2 | -
Peripheral motor neuropathy | 11 | 2 | - | 4 | <1 | -
General disorders and administration site conditions
Pyrexia | 27 | 3 | <1 | 22 | 2 | -
Musculoskeletal and connective tissue disorders
Bone pain | 19 | <1 | - | 10 | <1 | -
Back pain | 13 | <1 | - | 7 | - | -
Skin and subcutaneous tissue disorders
Rashes, eruptions and exanthems [Grouped term includes rash maculo-papular, rash macular, rash, rash papular, rash generalized, and rash vesicular.] | 13 | <1 | <1 | 8 | <1 | -
Respiratory, thoracic and mediastinal disorders
Dyspnea | 12 | 1 | - | 19 | 2 | -
Investigations
Decreased weight | 22 | <1 | - | 6 | <1 | -
Increased alanine aminotransferase | 10 | 3 | - | 4 | <1 | -
Metabolism and nutrition disorders
Decreased appetite | 18 | <1 | - | 12 | <1 | -
Psychiatric disorders
Insomnia | 19 | <1 | - | 12 | <1 | -
AVD = doxorubicin, vinblastine, and dacarbazine
ABVD = doxorubicin, bleomycin, vinblastine, and dacarbazine
Events were graded using the NCI CTCAE Version 4.03
Events listed are those having a ≥5% difference in rate between treatment arms

Previously Untreated High Risk Classical Hodgkin Lymphoma (cHL)

Study 7: AHOD1331

The safety of ADCETRIS was evaluated in Study 7: AHOD1331 [see Clinical Studies (14.1)]. The study included pediatric patients with previously untreated high risk cHL. Patients received ADCETRIS plus AVEPC chemotherapy at 1.8 mg/kg intravenously over 30 minutes prior to other chemotherapy in 21-day cycles (n = 296) or ABVE-PC in 21-day cycles (n = 297). Among patients who received ADCETRIS in combination with AVEPC chemotherapy, the median number of treatment cycles was 5 (range, 1-5).

Serious adverse reactions occurred in 22% of patients who received ADCETRIS plus AVEPC chemotherapy. Serious adverse reactions in >2% of patients included hypotension (3%) and febrile neutropenia (3%).

Table 5: Grade 3 or 4 Adverse Reactions Reported in ≥2% of ADCETRIS + AVEPC Treated Pediatric Patients with Previously Untreated High Risk Classical Hodgkin Lymphoma in Study 7: AHOD1331
 | ADCETRIS + AVEPC Total N = 296 % of patients |  | ABVE-PC Total N = 297 % of patients
System Organ Class Preferred Term | Grade 3 | Grade 4 | Grade 3 | Grade 4
Blood and lymphatic system disorders
Anemia | 35 | 1.7 | 28 | 2
Febrile neutropenia | 28 | 3.4 | 31 | 1.7
Lymphopenia | 13 | 11 | 8 | 18
Thrombocytopenia [Includes thrombocytopenia and platelet count decreased] | 10 | 22 | 11 | 16
Neutropenia | 8 | 43 | 4.4 | 36
Gastrointestinal disorders
Stomatitis | 10 | - | 7 | -
Nausea | 3.7 | - | 2 | -
Vomiting | 3.7 | - | 1.3 | -
Diarrhea | 2.4 | - | 0.3 | -
Colitis | 2 | 0.3 | 1 | -
Infections and infestations
Infections [Includes sepsis, device related infection, skin infection, enterocolitis infectious, pneumonia, appendicitis, cellulitis, urinary tract infection, candida infection, mucosal infection, vaginal infection, wound infection, anorectal infection, arteritis infective, bacteremia, catheter site infection, clostridium difficile colitis, gastroenteritis norovirus, gingivitis, H1N1 influenza, herpes simplex reactivation, infective myositis, klebsiella bacteremia, klebsiella sepsis, meningitis, esophageal infection, oral candidiasis, osteomyelitis, otitis media, septic shock, serratia infection, sinusitis, soft tissue infection, staphylococcal infection, vulvitis] | 9 | 2.7 | 7 | 3.4
Nervous system disorders
Peripheral sensory neuropathy | 6 | - | 4.4 | -
Metabolism and nutrition disorders
Hypokalemia | 5 | 0.7 | 6 | 1
Hyponatremia | 3.4 | - | 3 | -
Decreased appetite | 2.7 | - | 1.7 | -
Dehydration | 2.7 | - | 1 | -
Hepatobiliary disorders
Alanine aminotransferase increased | 3.7 | 0.3 | 2.7 | 0.3
General disorders and administration site conditions
Infusion-related reactions [Includes anaphylactic reaction, hypersensitivity, drug hypersensitivity, infusion-related reaction, and bronchospasm] | 3 | 1 | 5 | 1

Classical Hodgkin Lymphoma Post-Auto-HSCT Consolidation (Study 3: AETHERA)
ADCETRIS was studied in 329 patients with cHL at high risk of relapse or progression post-auto-HSCT in a randomized, double-blind, placebo-controlled clinical trial in which the recommended starting dose and schedule was 1.8 mg/kg of ADCETRIS administered intravenously over 30 minutes every 3 weeks or placebo for up to 16 cycles. Of the 329 enrolled patients, 327 (167 ADCETRIS, 160 placebo) received at least one dose of study treatment. The median number of treatment cycles in each study arm was 15 (range, 1–16) and 80 patients (48%) in the ADCETRIS-treatment arm received 16 cycles [see Clinical Studies (14.1)].

Standard international guidelines were followed for infection prophylaxis for herpes simplex virus (HSV), varicella-zoster virus (VZV), and Pneumocystis jiroveci pneumonia (PJP) post-auto-HSCT. Overall, 312 patients (95%) received HSV and VZV prophylaxis with a median duration of 11.1 months (range, 0–20) and 319 patients (98%) received PJP prophylaxis with a median duration of 6.5 months (range, 0–20).

Adverse reactions that led to dose delays in more than 5% of ADCETRIS-treated patients were neutropenia (22%), peripheral sensory neuropathy (16%), upper respiratory tract infection (6%), and peripheral motor neuropathy (6%) [see Dosage and Administration (2.3)]. Adverse reactions led to treatment discontinuation in 32% of ADCETRIS-treated patients. Adverse reactions that led to treatment discontinuation in 2 or more patients were peripheral sensory neuropathy (14%), peripheral motor neuropathy (7%), acute respiratory distress syndrome (1%), paresthesia (1%), and vomiting (1%). Serious adverse reactions were reported in 25% of ADCETRIS-treated patients. The most common serious adverse reactions were pneumonia (4%), pyrexia (4%), vomiting (3%), nausea (2%), hepatotoxicity (2%), and peripheral sensory neuropathy (2%).

Table 6: Adverse Reactions Reported in ≥10% in ADCETRIS-Treated Patients with Classical Hodgkin Lymphoma Post-Auto-HSCT Consolidation (Study 3: AETHERA)
 | ADCETRIS Total N = 167 % of patients |  |  | Placebo Total N = 160 % of patients
Body System Adverse Reaction | Any Grade | Grade 3 | Grade 4 | Any Grade | Grade 3 | Grade 4
Blood and lymphatic system disorders
Neutropenia [Derived from laboratory values and adverse reaction data] | 78 | 30 | 9 | 34 | 6 | 4
Thrombocytopenia | 41 | 2 | 4 | 20 | 3 | 2
Anemia | 27 | 4 | - | 19 | 2 | -
Nervous system disorders
Peripheral sensory neuropathy | 56 | 10 | - | 16 | 1 | -
Peripheral motor neuropathy | 23 | 6 | - | 2 | 1 | -
Headache | 11 | 2 | - | 8 | 1 | -
Infections and infestations
Upper respiratory tract infection | 26 | - | - | 23 | 1 | -
General disorders and administration site conditions
Fatigue | 24 | 2 | - | 18 | 3 | -
Pyrexia | 19 | 2 | - | 16 | - | -
Chills | 10 | - | - | 5 | - | -
Gastrointestinal disorders
Nausea | 22 | 3 | - | 8 | - | -
Diarrhea | 20 | 2 | - | 10 | 1 | -
Vomiting | 16 | 2 | - | 7 | - | -
Abdominal pain | 14 | 2 | - | 3 | - | -
Constipation | 13 | 2 | - | 3 | - | -
Respiratory, thoracic and mediastinal disorders
Cough | 21 | - | - | 16 | - | -
Dyspnea | 13 | - | - | 6 | - | 1
Investigations
Weight decreased | 19 | 1 | - | 6 | - | -
Musculoskeletal and connective tissue disorders
Arthralgia | 18 | 1 | - | 9 | - | -
Muscle spasms | 11 | - | - | 6 | - | -
Myalgia | 11 | 1 | - | 4 | - | -
Skin and subcutaneous tissue disorders
Pruritus | 12 | 1 | - | 8 | - | -
Metabolism and nutrition disorders
Decreased appetite | 12 | 1 | - | 6 | - | -
Events were graded using the NCI CTCAE Version 4

Relapsed Classical Hodgkin Lymphoma (Study 1)

ADCETRIS was studied in 102 patients with cHL in a single arm clinical trial in which the recommended starting dose and schedule was 1.8 mg/kg intravenously every 3 weeks. Median duration of treatment was 9 cycles (range, 1–16) [see Clinical Studies (14.1)].

Adverse reactions that led to dose delays in more than 5% of ADCETRIS-treated patients were neutropenia (16%) and peripheral sensory neuropathy (13%) [see Dosage and Administration (2.3)]. Adverse reactions led to treatment discontinuation in 20% of ADCETRIS-treated patients. Adverse reactions that led to treatment discontinuation in 2 or more patients were peripheral sensory neuropathy (6%) and peripheral motor neuropathy (3%). Serious adverse reactions were reported in 25% of ADCETRIS-treated patients. The most common serious adverse reactions were peripheral motor neuropathy (4%), abdominal pain (3%), pulmonary embolism (2%), pneumonitis (2%), pneumothorax (2%), pyelonephritis (2%), and pyrexia (2%).

Table 7: Adverse Reactions Reported in ≥10% of Patients with Relapsed Classical Hodgkin Lymphoma (Study 1)
 | cHL; Total N = 102 % of patients
Body System Adverse Reaction | Any Grade | Grade 3 | Grade 4
Blood and lymphatic system disorders
Neutropenia [Derived from laboratory values and adverse reaction data] | 54 | 15 | 6
Anemia | 33 | 8 | 2
Thrombocytopenia | 28 | 7 | 2
Lymphadenopathy | 11 | - | -
Nervous system disorders
Peripheral sensory neuropathy | 52 | 8 | -
Peripheral motor neuropathy | 16 | 4 | -
Headache | 19 | - | -
Dizziness | 11 | - | -
General disorders and administration site conditions
Fatigue | 49 | 3 | -
Pyrexia | 29 | 2 | -
Chills | 13 | - | -
Infections and infestations
Upper respiratory tract infection | 47 | - | -
Gastrointestinal disorders
Nausea | 42 | - | -
Diarrhea | 36 | 1 | -
Abdominal pain | 25 | 2 | 1
Vomiting | 22 | - | -
Constipation | 16 | - | -
Skin and subcutaneous tissue disorders
Rash | 27 | - | -
Pruritus | 17 | - | -
Alopecia | 13 | - | -
Night sweats | 12 | - | -
Respiratory, thoracic and mediastinal disorders
Cough | 25 | - | -
Dyspnea | 13 | 1 | -
Oropharyngeal pain | 11 | - | -
Musculoskeletal and connective tissue disorders
Arthralgia | 19 | - | -
Myalgia | 17 | - | -
Back pain | 14 | - | -
Pain in extremity | 10 | - | -
Psychiatric disorders
Insomnia | 14 | - | -
Anxiety | 11 | 2 | -
Metabolism and nutrition disorders
Decreased appetite | 11 | - | -
Events were graded using the NCI CTCAE Version 3.0

Previously Untreated Systemic Anaplastic Large Cell Lymphoma or Other CD30-Expressing Peripheral T-Cell Lymphomas (Study 6, ECHELON-2)

ADCETRIS in combination with CHP was evaluated in patients with previously untreated, CD30-expressing PTCL in a multicenter randomized, double-blind, double dummy, actively controlled trial. Patients were randomized to receive ADCETRIS + CHP or CHOP for 6 to 8, 21-day cycles. ADCETRIS was administered on Day 1 of each cycle, with a starting dose of 1.8 mg/kg intravenously over 30 minutes, approximately 1 hour after completion of CHP [see Clinical Studies (14.2)]. The trial required hepatic transaminases ≤3 times upper limit of normal (ULN), total bilirubin ≤1.5 times ULN, and serum creatinine ≤2 times ULN and excluded patients with Grade 2 or higher peripheral neuropathy.

A total of 449 patients were treated (223 with ADCETRIS + CHP, 226 with CHOP), with 6 cycles planned in 81%. In the ADCETRIS + CHP arm, 70% of patients received 6 cycles, and 18% received 8 cycles. Primary prophylaxis with G-CSF was administered to 34% of ADCETRIS + CHP-treated patients and 27% of CHOP-treated patients.

Fatal adverse reactions occurred in 3% of patients in the A+CHP arm and in 4% of patients in the CHOP arms, most often from infection. Serious adverse reactions were reported in 38% of ADCETRIS + CHP- treated patients and 35% of CHOP-treated patients. Serious adverse reactions occurring in >2% of ADCETRIS + CHP-treated patients included febrile neutropenia (14%), pneumonia (5%), pyrexia (4%), and sepsis (3%).

The most common adverse reactions observed ≥2% more in recipients of ADCETRIS + CHP were nausea, diarrhea, fatigue or asthenia, mucositis, pyrexia, vomiting, and anemia. Other common (≥10%) adverse reactions observed ≥2% more with ADCETRIS + CHP were febrile neutropenia, abdominal pain, decreased appetite, dyspnea, edema, cough, dizziness, hypokalemia, decreased weight, and myalgia.

In recipients of ADCETRIS + CHP, adverse reactions led to dose delays of ADCETRIS in 25% of patients, dose reduction in 9% (most often for peripheral neuropathy), and discontinuation of ADCETRIS with or without the other components in 7% (most often from peripheral neuropathy and infection).

Table 8: Adverse Reactions Reported in ≥10% of ADCETRIS + CHP-Treated Patients with Previously Untreated, CD30-Expressing PTCL (Study 6: ECHELON-2)
 | ADCETRIS + CHP Total N = 223 % of patients |  |  | CHOP Total N = 226 % of patients
Body System Adverse Reaction | Any Grade | Grade 3 | Grade 4 | Any Grade | Grade 3 | Grade 4
Blood and lymphatic system disorders
Anemia [Derived from laboratory values and adverse reaction data. Laboratory values were obtained at the start of each cycle and end of treatment.] | 66 | 13 | <1 | 59 | 12 | <1
Neutropenia | 59 | 17 | 22 | 58 | 14 | 22
Lymphopenia | 51 | 18 | 1 | 57 | 19 | 2
Febrile neutropenia | 19 | 17 | 2 | 16 | 12 | 4
Thrombocytopenia | 17 | 3 | 3 | 13 | 3 | 2
Gastrointestinal disorders
Nausea | 46 | 2 | - | 39 | 2 | -
Diarrhea | 38 | 6 | - | 20 | <1 | -
Mucositis | 30 | 2 | <1 | 27 | 3 | -
Constipation | 29 | <1 | <1 | 30 | 1 | -
Vomiting | 26 | <1 | - | 17 | 2 | -
Abdominal pain | 17 | 1 | - | 13 | <1 | -
Nervous system disorders
Peripheral neuropathy | 52 | 3 | <1 | 55 | 4 | -
Headache | 15 | <1 | - | 15 | <1 | -
Dizziness | 13 | - | - | 9 | <1 | -
General disorders and administration site conditions
Fatigue or asthenia | 35 | 2 | - | 29 | 2 | -
Pyrexia | 26 | 1 | <1 | 19 | - | -
Edema | 15 | <1 | - | 12 | <1 | -
Infections and infestations
Upper respiratory tract infection | 14 | <1 | - | 15 | <1 | -
Skin and subcutaneous disorders
Alopecia | 26 | - | - | 25 | 1 | -
Rash | 16 | 1 | <1 | 14 | 1 | -
Musculoskeletal and connective tissue disorders
Myalgia | 11 | - | - | 8 | - | -
Respiratory, thoracic and mediastinal disorders
Dyspnea | 15 | 2 | - | 11 | 2 | -
Cough | 13 | <1 | - | 10 | - | -
Metabolism and nutrition disorders
Decreased appetite | 17 | 1 | - | 12 | 1 | -
Hypokalemia | 12 | 4 | - | 8 | <1 | <1
Investigations
Weight decreased | 12 | <1 | - | 8 | <1 | -
Psychiatric disorders
Insomnia | 11 | - | - | 14 | - | -
The table includes a combination of grouped and ungrouped terms. CHP = cyclophosphamide, doxorubicin, and prednisone; CHOP = cyclophosphamide, doxorubicin, vincristine, and prednisone
Events were graded using the NCI CTCAE Version 4.03

Relapsed Systemic Anaplastic Large Cell Lymphoma (Study 2)

ADCETRIS was studied in 58 patients with sALCL in a single arm clinical trial in which the recommended starting dose and schedule was 1.8 mg/kg intravenously every 3 weeks. Median duration of treatment was 7 cycles (range, 1–16) [see Clinical Studies (14.2)].

Adverse reactions that led to dose delays in more than 5% of ADCETRIS-treated patients were neutropenia (12%) and peripheral sensory neuropathy (7%) [see Dosage and Administration (2.3)]. Adverse reactions led to treatment discontinuation in 19% of ADCETRIS-treated patients. The adverse reaction that led to treatment discontinuation in 2 or more patients was peripheral sensory neuropathy (5%). Serious adverse reactions were reported in 41% of ADCETRIS-treated patients. The most common serious adverse reactions were septic shock (3%), supraventricular arrhythmia (3%), pain in extremity (3%), and urinary tract infection (3%).

Table 9: Adverse Reactions Reported in ≥10% of Patients with Relapsed Systemic Anaplastic Large Cell Lymphoma (Study 2)
 | sALCL Total N = 58 % of patients
Body System Adverse Reaction | Any Grade | Grade 3 | Grade 4
Blood and lymphatic system disorders
Neutropenia [Derived from laboratory values and adverse reaction data] | 55 | 12 | 9
Anemia | 52 | 2 | -
Thrombocytopenia | 16 | 5 | 5
Lymphadenopathy | 10 | - | -
Nervous system disorders
Peripheral sensory neuropathy | 53 | 10 | -
Headache | 16 | 2 | -
Dizziness | 16 | - | -
General disorders and administration site conditions
Fatigue | 41 | 2 | 2
Pyrexia | 38 | 2 | -
Chills | 12 | - | -
Pain | 28 | - | 5
Edema peripheral | 16 | - | -
Infections and infestations
Upper respiratory tract infection | 12 | - | -
Gastrointestinal disorders
Nausea | 38 | 2 | -
Diarrhea | 29 | 3 | -
Vomiting | 17 | 3 | -
Constipation | 19 | 2 | -
Skin and subcutaneous tissue disorders
Rash | 31 | - | -
Pruritus | 19 | - | -
Alopecia | 14 | - | -
Dry skin | 10 | - | -
Respiratory, thoracic and mediastinal disorders
Cough | 17 | - | -
Dyspnea | 19 | 2 | -
Musculoskeletal and connective tissue disorders
Myalgia | 16 | 2 | -
Back pain | 10 | 2 | -
Pain in extremity | 10 | 2 | 2
Muscle spasms | 10 | 2 | -
Psychiatric disorders
Insomnia | 16 | - | -
Metabolism and nutrition disorders
Decreased appetite | 16 | 2 | -
Investigations
Weight decreased | 12 | 3 | -
Events were graded using the NCI CTCAE Version 3.0

Primary Cutaneous Anaplastic Large Cell Lymphoma and CD30-Expressing Mycosis Fungoides (Study 4: ALCANZA)

ADCETRIS was studied in 131 patients with pcALCL or CD30-expressing MF requiring systemic therapy in a randomized, open-label, multicenter clinical trial in which the recommended starting dose and schedule was ADCETRIS 1.8 mg/kg intravenously over 30 minutes every 3 weeks or physician’s choice of either methotrexate 5 to 50 mg orally weekly or bexarotene 300 mg/m^2 orally daily.

Of the 131 enrolled patients, 128 (66 brentuximab vedotin, 62 physician’s choice) received at least one dose of study treatment. The median number of treatment cycles in the ADCETRIS treatment arm was 12 (range, 1–16) compared to 3 (range, 1–16) and 6 (range, 1–16) in the methotrexate and bexarotene arms, respectively. Twenty-four (24) patients (36%) in the ADCETRIS-treatment arm received 16 cycles compared to 5 patients (8%) in the physician’s choice arm [see Clinical Studies (14.2)].

Adverse reactions that led to dose delays in more than 5% of ADCETRIS-treated patients were peripheral sensory neuropathy (15%) and neutropenia (6%) [see Dosage and Administration (2.3)]. Adverse reactions led to treatment discontinuation in 24% of ADCETRIS-treated patients. The most common adverse reaction that led to treatment discontinuation was peripheral neuropathy (12%). Serious adverse reactions were reported in 29% of ADCETRIS-treated patients. The most common serious adverse reactions were cellulitis (3%) and pyrexia (3%).

Table 10: Adverse Reactions Reported in ≥10% ADCETRIS-Treated Patients with pcALCL or CD30-Expressing MF (Study 4: ALCANZA)
 | ADCETRIS Total N = 66 % of patients |  |  | Physician’s Choice [Physician’s choice of either methotrexate or bexarotene] Total N = 62 % of patients
Body System Adverse Reaction | Any Grade | Grade 3 | Grade 4 | Any Grade | Grade 3 | Grade 4
Blood and lymphatic system disorders
Anemia [Derived from laboratory values and adverse reaction data] | 62 | - | - | 65 | 5 | -
Neutropenia | 21 | 3 | 2 | 24 | 5 | -
Thrombocytopenia | 15 | 2 | 2 | 2 | - | -
Nervous system disorders
Peripheral sensory neuropathy | 45 | 5 | - | 2 | - | -
Gastrointestinal disorders
Nausea | 36 | 2 | - | 13 | - | -
Diarrhea | 29 | 3 | - | 6 | - | -
Vomiting | 17 | 2 | - | 5 | - | -
General disorders and administration site conditions
Fatigue | 29 | 5 | - | 27 | 2 | -
Pyrexia | 17 | - | - | 18 | 2 | -
Edema peripheral | 11 | - | - | 10 | - | -
Asthenia | 11 | 2 | - | 8 | - | 2
Skin and subcutaneous tissue disorders
Pruritus | 17 | 2 | - | 13 | 3 | -
Alopecia | 15 | - | - | 3 | - | -
Rash maculo-papular | 11 | 2 | - | 5 | - | -
Pruritus generalized | 11 | 2 | - | 2 | - | -
Metabolism and nutrition disorders
Decreased appetite | 15 | - | - | 5 | - | -
Musculoskeletal and connective tissue disorders
Arthralgia | 12 | - | - | 6 | - | -
Myalgia | 12 | - | - | 3 | - | -
Respiratory, thoracic and mediastinal disorders
Dyspnea | 11 | - | - | - | - | -
Events were graded using the NCI CTCAE Version 4.03

Relapsed or Refractory Large B-Cell Lymphoma (Study 8: ECHELON-3)

The safety of ADCETRIS in combination with lenalidomide and a rituximab product was evaluated in ECHELON-3, a randomized, multicenter, double-blind, placebo-controlled trial in patients with relapsed or refractory LBCL who had received at least 2 prior lines of systemic therapy and who were not eligible for HSCT or CAR T-cell therapy [see Clinical Studies (14.5)].

Patients in the treatment arm (n = 112) received ADCETRIS, 1.2 mg/kg via intravenous infusion every 3 weeks, lenalidomide, and a rituximab product. Placebo replaced ADCETRIS in the placebo plus lenalidomide and rituximab arm (n = 116).

The trial required an absolute neutrophil count ≥1,000/µL, platelet count ≥50,000/µL, creatinine clearance (CrCL) ≥45 mL/min, hepatic transaminases ≤3 times the upper limit of normal (ULN), and bilirubin <1.5 times ULN. The trial excluded patients having Eastern Cooperative Oncology Group (ECOG) performance status above 2, active central nervous system (CNS) lymphoma, and Grade 2 or higher peripheral neuropathy. Granulocyte colony-stimulating factor (G-CSF) primary prophylaxis was required and administered to 98% of patients in the ADCETRIS plus lenalidomide and rituximab arm and 91% of patients in the lenalidomide and rituximab arm.

The median age was 71 years (range: 21 to 89 years); 44% of patients were female; 53% were White, 26% were Asian, and 4% were Hispanic or Latino. There were no Black or African American patients enrolled in ECHELON-3. Among patients who received ADCETRIS, the median number of treatment cycles was 5 (range, 1-34).

Serious adverse reactions occurred in 60% of patients who received ADCETRIS in combination with lenalidomide and a rituximab product. Serious adverse reactions that occurred in >2% of patients included pneumonia (21%), COVID-19 (13%, includes COVID-19 pneumonia), sepsis (9%), febrile neutropenia (7%), hemorrhage (3.6%), urinary tract infection (3.6%), thrombocytopenia (2.7%) and upper respiratory tract infection (2.7%). Fatal adverse reactions occurred in 12% of patients who received ADCETRIS in combination with lenalidomide and a rituximab product, including COVID-19 (4.5%, includes COVID-19 pneumonia), pneumonia (3.6%), and sepsis (1.8%).

Adverse reactions led to dose reduction of ADCETRIS in 6% of patients, all due to peripheral neuropathy. Adverse reactions leading to dose delay of ADCETRIS in more than 5% of patients included neutropenia (23%), COVID-19 (13%), pneumonia (8%), and thrombocytopenia (8%).

Adverse reactions led to discontinuation of ADCETRIS in 20% of patients. Adverse reactions that led to treatment discontinuation in 3 or more patients included peripheral neuropathy (4.5%) and pneumonia (2.7%).

Table 11: Adverse Reactions Reported in ≥10% of ADCETRIS in Combination with Lenalidomide and a Rituximab Product-Treated Patients in Relapsed or Refractory LBCL (Study 8: ECHELON-3)
 | ADCETRIS + Lenalidomide + Rituximab N = 112 |  | Placebo + Lenalidomide + Rituximab N = 116
Body System Adverse Reaction | All Grades % | Grade 3-4 % | All Grades % | Grade 3-4 %
General disorders and Administration Site Conditions
Fatigue [Includes other related terms.] | 46 | 10 | 29 | 5
Pyrexia | 15 | 1.8 | 15 | 0.9
Gastrointestinal disorders
Diarrhea | 31 | 4.5 | 23 | 1.7
Constipation | 17 | 1.8 | 18 | 0
Nausea | 15 | 0.9 | 16 | 0.9
Abdominal pain | 12 | 1.8 | 12 | 1.7
Stomatitis | 11 | 0 | 7 | 0
Nervous system disorders
Peripheral neuropathy [Includes peripheral sensory neuropathy, peripheral motor neuropathy, paresthesia, hypoesthesia, neuropathy peripheral, hypoesthesia oral, oral dysesthesia, neuralgia, paresthesia oral.] | 27 | 5 | 21 | 0
Infections and Infestations
COVID-19 [Includes COVID-19 and COVID-19 pneumonia.] | 27 | 13 | 16 | 8
Pneumonia [Includes pneumonia, COVID-19 pneumonia, atypical pneumonia, bronchopulmonary aspergillosis, lung infiltration, organizing pneumonia, pneumocystis jirovecii pneumonia, pneumonia bacterial, pneumonia fungal, pneumonia streptococcal, pneumonia viral.] | 27 | 21 | 10 | 9
Upper respiratory tract infection | 12 | 2.7 | 5 | 0
Skin and subcutaneous tissue disorders
Rash | 27 | 2.7 | 16 | 0.9
Pruritus | 17 | 0 | 6 | 0
Renal and urinary disorders
Renal insufficiency | 20 | 3.6 | 14 | 4.3
Respiratory, thoracic and mediastinal disorders
Cough | 17 | 0 | 9 | 0
Dyspnea | 12 | 0.9 | 14 | 2.6
Metabolism and nutrition disorders
Decreased appetite | 17 | 0.9 | 9 | 0
Investigations
Weight decreased | 13 | 0.9 | 5 | 0.9

Clinically relevant adverse reactions in <10% of patients who received ADCETRIS in combination with lenalidomide and a rituximab product include febrile neutropenia, edema, hypotension, urinary tract infection, sepsis, respiratory tract infection, vomiting, back pain, dizziness, arthralgia, herpes virus infection, bone pain, atrial fibrillation or flutter, lower respiratory tract infection, and cardiac failure.

Table 12: Select Laboratory Abnormalities (≥20%) that Worsened from Baseline in Patients Who Received ADCETRIS + Lenalidomide + Rituximab-Treated Patients in Relapsed or Refractory LBCL (Study 8: ECHELON-3)
 | ADCETRIS + Lenalidomide + Rituximab N = 112 [The denominator used to calculate the rate varied from 105 to 107 in the ADCETRIS + lenalidomide + rituximab arm, and from 97 to 103 in the placebo + lenalidomide + rituximab arm based on the number of patients with a baseline value and at least one post-treatment value.] |  | Placebo + Lenalidomide + Rituximab N = 116
Laboratory Abnormality | All Grades (%) | Grade 3-4 (%) | All Grades (%) | Grade 3-4 (%)
Hematology
Neutrophils decreased | 77 | 49 | 63 | 42
Lymphocytes decreased | 65 | 38 | 53 | 30
Platelets decreased | 65 | 29 | 54 | 18
Hemoglobin decreased | 54 | 19 | 49 | 14
Chemistry
Alanine aminotransferase increased | 31 | 0.9 | 17 | 0
Potassium decreased | 31 | 7 | 29 | 2.9
Albumin decreased | 29 | 0.9 | 25 | 1
Creatinine increased | 26 | 2.8 | 23 | 0
Calcium decreased | 21 | 0.9 | 7 | 0

Additional Important Adverse Reactions

Infusion reactions

In studies of ADCETRIS as monotherapy (Studies 1–4), 13% of ADCETRIS-treated patients experienced infusion-related reactions. The most common adverse reactions in Studies 1–4 (≥3% in any study) associated with infusion-related reactions were chills (4%), nausea (3–4%), dyspnea (2–3%), pruritus (2–5%), pyrexia (2%), and cough (2%). Grade 3 events were reported in 5 of the 51 ADCETRIS-treated patients who experienced infusion-related reactions.

In a study of ADCETRIS in combination with AVD (Study 5, ECHELON-1), infusion-related reactions were reported in 57 patients (9%) in the ADCETRIS + AVD-treated arm. Grade 3 events were reported in 3 of the 57 patients treated with ADCETRIS + AVD who experienced infusion-related reactions. The most common adverse reaction (≥2%) associated with infusion-related reactions was nausea (2%).

In a study of ADCETRIS in combination with CHP (Study 6, ECHELON-2), infusion-related reactions were reported in 10 patients (4%) in the ADCETRIS + CHP-treated arm: 2 (1%) patients with events that were Grade 3 or higher events, and 8 (4%) patients with events that were less than Grade 3.

In a study of ADCETRIS in combination with lenalidomide and rituximab (Study 8, ECHELON-3), Grade 1 or 2 infusion-related reactions were reported in 6 patients (5%) in the ADCETRIS + lenalidomide + rituximab arm.

Pulmonary toxicity

In a trial in patients with cHL that studied ADCETRIS with bleomycin as part of a combination regimen, the rate of non-infectious pulmonary toxicity was higher than the historical incidence reported with ABVD (doxorubicin, bleomycin, vinblastine, dacarbazine). Patients typically reported cough and dyspnea. Interstitial infiltration and/or inflammation were observed on radiographs and computed tomographic imaging of the chest. Most patients responded to corticosteroids. The concomitant use of ADCETRIS with bleomycin is contraindicated [see Contraindications (4)].

In a study of ADCETRIS in combination with AVD (Study 5, ECHELON-1), non-infectious pulmonary toxicity events were reported in 12 patients (2%) in the ADCETRIS + AVD arm. These events included lung infiltration (6 patients) and pneumonitis (6 patients), or interstitial lung disease (1 patient).

In a study of ADCETRIS in combination with CHP (Study 6, ECHELON-2), non-infectious pulmonary toxicity events were reported in 5 patients (2%) in the ADCETRIS + CHP arm; all 5 events were pneumonitis. Cases of pulmonary toxicity have also been reported in patients receiving ADCETRIS monotherapy. In Study 3 (AETHERA), pulmonary toxicity was reported in 8 patients (5%) in the ADCETRIS-treated arm and 5 patients (3%) in the placebo arm.

Immunogenicity: Anti-Drug Antibody-Associated Adverse Reactions

During treatment in patients with relapsed or refractory cHL and relapsed or refractory systemic ALCL in Studies 1 and 2, two of the patients (1%) with persistently positive antibodies experienced adverse reactions consistent with infusion reactions that led to discontinuation of treatment [see Warnings and Precautions (5.2)]. Overall, a higher incidence of infusion-related reactions was observed in patients who developed persistently positive antibodies [see Clinical Pharmacology (12.6)].

6.2 Post Marketing Experience

The following adverse reactions have been identified during post-approval use of ADCETRIS. Because these reactions are reported voluntarily from a population of uncertain size, it is not always possible to reliably estimate their frequency or establish a causal relationship to drug exposure.

Blood and lymphatic system disorders: febrile neutropenia [see Warnings and Precautions (5.3)].

Gastrointestinal disorders: acute pancreatitis and gastrointestinal complications (including fatal outcomes) [see Warnings and Precautions (5.12)].

Hepatobiliary disorders: hepatotoxicity [see Warnings and Precautions (5.8)].

Infections: PML [see Boxed Warning, Warnings and Precautions (5.9)], serious infections and opportunistic infections [see Warnings and Precautions (5.4)].

Metabolism and nutrition disorders: hyperglycemia [see Warnings and Precautions (5.13)].

Respiratory, thoracic and mediastinal disorders: noninfectious pulmonary toxicity including pneumonitis, interstitial lung disease, and ARDS (some with fatal outcomes) [see Warnings and Precautions (5.10) and Adverse Reactions (6.1)].

Skin and subcutaneous tissue disorders: Toxic epidermal necrolysis, including fatal outcomes [see Warnings and Precautions (5.11)].

7 DRUG INTERACTIONS

7.1 Effect of Other Drugs on ADCETRIS

CYP3A4 Inhibitors: Co-administration of ADCETRIS with ketoconazole, a potent CYP3A4 inhibitor, increased exposure to MMAE [see Clinical Pharmacology (12.3)], which may increase the risk of adverse reaction. Closely monitor adverse reactions when ADCETRIS is given concomitantly with strong CYP3A4 inhibitors.

8 USE IN SPECIFIC POPULATIONS

8.1 Pregnancy

Risk Summary

ADCETRIS can cause fetal harm based on the findings from animal studies and the drug’s mechanism of action [see Clinical Pharmacology (12.1)]. In animal reproduction studies, administration of brentuximab vedotin to pregnant rats during organogenesis at doses similar to the clinical dose of 1.8 mg/kg every three weeks caused embryo-fetal toxicities, including congenital malformations (see Data). The available data from case reports on ADCETRIS use in pregnant women are insufficient to inform a drug-associated risk of adverse developmental outcomes. Advise a pregnant woman of the potential risk to a fetus.

The estimated background risk of major birth defects and miscarriage for the indicated population is unknown. All pregnancies have a background risk of birth defect, loss, or other adverse outcomes. In the U.S. general population, the estimated background risk of major birth defects and miscarriage in clinically recognized pregnancies is 2–4% and 15–20%, respectively.

Data

Animal Data

In an embryo-fetal developmental study, pregnant rats received 2 intravenous doses of 0.3, 1, 3, or 10 mg/kg brentuximab vedotin during the period of organogenesis (once each on Pregnancy Days 6 and 13). Drug-induced embryo-fetal toxicities were seen mainly in animals treated with 3 and 10 mg/kg of the drug and included increased early resorption (≥99%), post-implantation loss (≥99%), decreased numbers of live fetuses, and external malformations (i.e., umbilical hernias and malrotated hindlimbs). Systemic exposure in animals at the brentuximab vedotin dose of 3 mg/kg is approximately the same exposure in patients with cHL or sALCL who received the recommended dose of 1.8 mg/kg every three weeks.

8.2 Lactation

Risk Summary

There is no information regarding the presence of brentuximab vedotin in human milk, the effects on the breastfed child, or the effects on milk production. Because of the potential for serious adverse reactions in a breastfed child from ADCETRIS, including cytopenias and neurologic or gastrointestinal toxicities, advise patients that breastfeeding is not recommended during ADCETRIS treatment.

8.3 Females and Males of Reproductive Potential

ADCETRIS can cause fetal harm based on the findings from animal studies and the drug’s mechanism of action [see Use in Specific Populations (8.1)].

Pregnancy Testing

Verify the pregnancy status of females of reproductive potential prior to initiating ADCETRIS therapy.

Contraception

Females

Advise females of reproductive potential to use effective contraception during ADCETRIS treatment and for 2 months after the last dose of ADCETRIS. Advise females to immediately report pregnancy [see Use in Specific Populations (8.1)].

Males

ADCETRIS may damage spermatozoa and testicular tissue, resulting in possible genetic abnormalities. Males with female sexual partners of reproductive potential should use effective contraception during ADCETRIS treatment and for 4 months after the last dose of ADCETRIS [see Nonclinical Toxicology (13.1)].

Infertility

Females

Based on findings in animal studies with MMAE-containing antibody-drug conjugates (ADCs), ADCETRIS may impair female fertility. The effect on fertility is reversible [see Nonclinical Toxicology (13.1)].

Males

Based on findings in rats, male fertility may be compromised by treatment with ADCETRIS [see Nonclinical Toxicology (13.1)].

8.4 Pediatric Use

The safety and effectiveness of ADCETRIS have been established in pediatric patients age 2 years and older with previously untreated high risk classical Hodgkin lymphoma in combination with doxorubicin, vincristine, etoposide, prednisone, and cyclophosphamide. The safety and effectiveness of ADCETRIS have not been established for all other indications [see Indications and Usage (1)].

Previously Untreated, High Risk Classical Hodgkin Lymphoma (cHL) in Combination with Doxorubicin, Vincristine, Etoposide, Prednisone, and Cyclophosphamide

The safety and effectiveness of ADCETRIS have been established in pediatric patients 2 years and older with previously untreated high risk cHL in combination with doxorubicin, vincristine, etoposide, prednisone, and cyclophosphamide chemotherapy.

Use of ADCETRIS for this indication is supported by evidence from Study 7: AHOD1331, a randomized study which included pediatric patients with previously untreated high risk cHL, including patients in the following age groups: 9 patients 3 to less than 6 years of age, 81 patients 6 to less than 12 years of age, and 345 patients 12 to less than 17 years of age [see Adverse Reactions (6.1) and Clinical Studies (14.1)].

The safety and efficacy of ADCETRIS have not been established for this indication in patients younger than 2 years.

Previously Untreated High Risk Classical Hodgkin Lymphoma (cHL) in Combination with Etoposide, Prednisone, Doxorubicin, Cyclophosphamide, Prednisone, and Dacarbazine

The safety and effectiveness of ADCETRIS in combination with etoposide (E), prednisone (P), and doxorubicin (A)/cyclophosphamide (C), prednisone (P), and dacarbazine (Dac) (AEPA/CAPDac) were assessed but have not been established based on a single arm, open-label trial (NCT01920932) in 77 patients, which included 48 pediatric patients age 6 to less than 17 with previously untreated high risk (IIB, IIIB, IVA, or IVB) cHL. No new safety signals were identified in this study.

Relapsed or Refractory Classical HL (cHL)

ADCETRIS in Combination with Gemcitabine

The safety and effectiveness of ADCETRIS in combination with gemcitabine were assessed but have not been established based on a study (NCT01780662) in 45 patients, which included 18 pediatric patients age 5 to less than 17 with relapsed or refractory cHL. No new safety signals were identified in this study.

ADCETRIS Monotherapy

The safety and effectiveness of ADCETRIS monotherapy was assessed but have not been established based on a study (NCT01492088) in 36 patients, which included 15 pediatric patients age 8 to less than 17 with relapsed or refractory cHL. No new safety signals were identified in this study.

Relapsed or Refractory Systemic ALCL (sALCL)

ADCETRIS monotherapy

The safety and effectiveness of ADCETRIS monotherapy was assessed but have not been established based on a study (NCT01492088) in 36 patients, which included 16 pediatric patients age 7 to less than 17 with sALCL. No new safety signals were identified in this study.

Newly Diagnosed ALK+ ALCL

The safety and effectiveness of ADCETRIS in combination with alternating chemotherapy Courses A (dexamethasone, ifosfamide, methotrexate, etoposide, cytarabine) and B (dexamethasone, methotrexate, cyclophosphamide, doxorubicin) administered every 21 days for a total of 6 cycles was assessed but have not been established based on a study (NCT01979536) in 67 patients, which included 61 pediatric patients age 2 to less than 17 years with newly diagnosed ALK+ ALCL. No new safety signals were identified in this study.

8.5 Geriatric Use

In the clinical trial of ADCETRIS in combination with AVD for patients with previously untreated Stage III or IV cHL (Study 5: ECHELON-1), 9% of ADCETRIS + AVD-treated patients were age 65 and older. Older age was a risk factor for febrile neutropenia, occurring in 39% of patients who were age 65 and older versus 17% of patients less than age 65, who received ADCETRIS + AVD [see Dosage and Administration (2.3)]. The ECHELON-1 trial did not contain sufficient information on patients age 65 and older to determine whether they respond differently from younger patients [see Clinical Studies (14.1)].

In the clinical trial of ADCETRIS in combination with CHP for patients with previously untreated, CD30-expressing PTCL (Study 6: ECHELON-2), 31% of ADCETRIS + CHP-treated patients were age 65 and older [see Clinical Studies (14.2)]. Among older patients, 74% had adverse reactions ≥ Grade 3 and 49% had serious adverse reactions. Among patients younger than age 65, 62% had adverse reactions ≥ Grade 3 and 33% had serious adverse reactions. Older age was a risk factor for febrile neutropenia, occurring in 29% of patients who were age 65 and older versus 14% of patients less than age 65.

Other clinical trials of ADCETRIS in cHL (Study 1; Study 3: AETHERA) and sALCL (Study 2) did not include sufficient numbers of patients who were age 65 and older to determine whether they respond differently from younger patients [see Clinical Studies (14.1, 14.3)].

In the clinical trial of ADCETRIS in pcALCL or CD30-expressing MF (Study 4: ALCANZA), 42% of ADCETRIS-treated patients were age 65 and older [see Clinical Studies (14.4)]. No meaningful differences in safety or efficacy were observed between these patients and younger patients.

In the clinical trial of ADCETRIS in relapsed or refractory LBCL (Study 8: ECHELON-3) [see Clinical Studies (14.5)], 79 (71%) of ADCETRIS-treated patients were age 65 and older. No meaningful differences in safety or efficacy were observed between these patients and younger patients.

8.6 Renal Impairment

Avoid the use of ADCETRIS in patients with severe renal impairment (CrCL <30 mL/min) [see Warnings and Precautions (5.6) and Clinical Pharmacology (12.3)]. No dosage adjustment is required for mild (CrCL >50–80 mL/min) or moderate (CrCL 30–50 mL/min) renal impairment.

8.7 Hepatic Impairment

Avoid the use of ADCETRIS in patients with moderate (Child-Pugh B) or severe (Child-Pugh C) hepatic impairment [see Warnings and Precautions (5.7) and Clinical Pharmacology (12.3)]. Dosage reduction is required in patients with mild (Child-Pugh A) hepatic impairment [see Dosage and Administration (2.3)].

Hepatic impairment for patients with relapsed or refractory large B-cell lymphoma is defined per the National Cancer Institute Organ Dysfunction Working Group.

10 OVERDOSAGE

There is no known antidote for overdosage of ADCETRIS. In case of overdosage, the patient should be closely monitored for adverse reactions, particularly neutropenia, and supportive treatment should be administered.

11 DESCRIPTION

ADCETRIS (brentuximab vedotin) is a CD30-directed antibody and microtubule inhibitor conjugate consisting of three components: 1) the chimeric IgG1 antibody cAC10, specific for human CD30, 2) the microtubule disrupting agent MMAE, and 3) a protease-cleavable linker that covalently attaches MMAE to cAC10.

Brentuximab vedotin has an approximate molecular weight of 153 kDa. Approximately 4 molecules of MMAE are attached to each antibody molecule. Brentuximab vedotin is produced by chemical conjugation of the antibody and small molecule components. The antibody is produced by mammalian (Chinese hamster ovary) cells, and the small molecule components are produced by chemical synthesis.

ADCETRIS (brentuximab vedotin) for injection is supplied as a sterile, white to off-white, preservative-free lyophilized cake or powder in single-dose vials. Following reconstitution with 10.5 mL Sterile Water for Injection, USP, a solution containing 5 mg/mL brentuximab vedotin is produced. The reconstituted product contains 70 mg/mL trehalose dihydrate, 5.6 mg/mL sodium citrate dihydrate, 0.21 mg/mL citric acid monohydrate, and 0.20 mg/mL polysorbate 80 and water for injection. The pH is approximately 6.6.

12 CLINICAL PHARMACOLOGY

12.1 Mechanism of Action

CD30 is a member of the tumor necrosis factor receptor family and is expressed on the surface of sALCL cells and on Hodgkin Reed-Sternberg (HRS) cells in cHL. CD30 is variably expressed in other T-cell lymphomas. Expression of CD30 on healthy tissue and cells is limited. In vitro data suggest that signaling through CD30-CD30L binding may affect cell survival and proliferation.

Brentuximab vedotin is an antibody-drug conjugate (ADC). The antibody is a chimeric IgG1 directed against CD30. The small molecule, MMAE, is a microtubule-disrupting agent. MMAE is covalently attached to the antibody via a linker. Nonclinical data suggest that the anticancer activity of ADCETRIS is due to the binding of the ADC to CD30-expressing cells, followed by internalization of the ADC‑CD30 complex, and the release of MMAE via proteolytic cleavage. Binding of MMAE to tubulin disrupts the microtubule network within the cell, subsequently inducing cell cycle arrest and apoptotic death of the cells. Additionally, in vitro data provide evidence for antibody-dependent cellular phagocytosis (ADCP).

12.2 Pharmacodynamics

Cardiac Electrophysiology

At the recommended dose of 1.8 mg/kg, brentuximab vedotin had no large QTc prolongation (>10ms).

12.3 Pharmacokinetics

The pharmacokinetics of brentuximab vedotin were evaluated in monotherapy and combination chemotherapy in patients with hematological malignancies. The pharmacokinetics of brentuximab vedotin in combination therapy were similar to those in monotherapy. Total antibody and ADC had similar pharmacokinetic profiles. The pharmacokinetics of the ADC and MMAE are presented.

ADC

Maximum concentrations of ADC were observed near the end of infusion. Exposures were approximately dose proportional from 1.2 to 2.7 mg/kg (1.5 times the highest approved recommended dosage).

- 1.8 mg/kg Q3W: Steady state was achieved within 21 days, and minimal to no accumulation of ADC was observed.
- 1.2 mg/kg Q2W: Steady state was achieved within 56 days, 1.27-fold accumulation (14‑day AUC) was observed.
- 1.2 mg/kg Q3W: Steady state was achieved within 21 days, and minimal to no accumulation of ADC was observed.

MMAE

Maximum concentrations of MMAE were observed approximately 1 to 3 days after end of infusion. Exposures decreased with continued administration of ADCETRIS with approximately 50% to 80% of the exposure of the first dose observed at subsequent doses.

- 1.8 mg/kg Q3W: Steady state was achieved within 21 days.
- 1.2 mg/kg Q2W: Steady state was achieved within 56 days.
- 1.2 mg/kg Q3W: Steady state was achieved within 21 days.

Distribution

In humans, the mean steady state volume of distribution was approximately 6–10 L for ADC.

In vitro, the binding of MMAE to human plasma proteins ranged from 68–82%. MMAE is not likely to displace or to be displaced by highly protein-bound drugs.

Elimination

ADC elimination exhibited a multi-exponential decline with a t1/2 of approximately 4 to 6 days.

MMAE elimination exhibited a mono-exponential decline with a t1/2 of approximately 3 to 4 days. Elimination of MMAE appeared to be limited by its rate of release from ADC.

Metabolism

A small fraction of MMAE released from brentuximab vedotin is metabolized. In vitro data indicate that the MMAE metabolism that occurs is primarily via oxidation by CYP3A4/5.

Excretion

After a single dose of 1.8 mg/kg of ADCETRIS in patients, approximately 24% of the total MMAE administered was recovered in both urine and feces over a 1-week period, approximately 72% of which was recovered in the feces, and the majority was excreted unchanged.

Specific Populations

Sex and race do not have a meaningful effect on the pharmacokinetics of brentuximab vedotin.

Pediatric Patients

The pharmacokinetics of brentuximab vedotin and MMAE were evaluated in 65 pediatric patients aged 3 to <6 years (N=3), 6 to <12 years (N=30) and 12 to <17 years (N=32). Following the recommended dosage of brentuximab vedotin 1.8 mg/kg Q3W, the dose-normalized steady state Cavg of brentuximab vedotin in patients 12 to <17 years of age were generally consistent with those in adult patients administered brentuximab vedotin 1.2 mg/kg Q2W. The median AUC of ADC was 22% lower in patients 6 to <12 years of age (median [range] body weight = 28.8 kg [16.2, 80.8 kg]), and 37% lower in patients 3 to <6 years of age (median [range] body weight = 17.0 kg [10.7, 31.1 kg]), respectively, compared to that in patients 12 to <17 years of age (median [range] body weight = 52.7 kg [28.5, 123.9 kg]). The AUC of MMAE was 25% lower in patients 6 to <12 years of age, and 41% lower in patients 3 to <6 years of age, respectively, compared to that in patients 12 to <17 years of age. After accounting for body weight, other factors such as age, sex, race, and baseline albumin had no clinically significant effect on the PK of ADC and MMAE in pediatric patients 3 to <17 years of age.

Renal Impairment

The pharmacokinetics of brentuximab vedotin and MMAE were evaluated after the administration of 1.2 mg/kg of ADCETRIS to patients with mild (CrCL >50–80 mL/min; n=4), moderate (CrCL 30–50 mL/min; n=3) and severe (CrCL <30 mL/min; n=3) renal impairment. The AUC of MMAE was approximately 2-fold higher in patients with severe renal impairment compared to patients with normal renal function and not meaningfully altered in patients with mild or moderate renal impairment.

Hepatic Impairment

The pharmacokinetics of brentuximab vedotin and MMAE were evaluated after the administration of 1.2 mg/kg of ADCETRIS to patients with mild (Child-Pugh A; n=1), moderate (Child-Pugh B; n=5) and severe (Child-Pugh C; n=1) hepatic impairment. The AUC of MMAE was approximately 2.3-fold higher in patients with hepatic impairment compared to patients with normal hepatic function.

Drug Interaction Studies

Effects of Other Drugs on ADCETRIS

Co-administration of ADCETRIS with ketoconazole, a potent CYP3A4 inhibitor, increased exposure to MMAE by approximately 34%.

Co-administration of ADCETRIS with rifampin, a potent CYP3A4 inducer, reduced exposure to MMAE by approximately 46%.

Effects of ADCETRIS on Other Drugs

Co-administration of ADCETRIS did not affect exposure to midazolam, a CYP3A4 substrate.

In vitro studies using human liver microsomes indicate that MMAE inhibits CYP3A4/5 but not other CYP450 isoforms. MMAE did not induce any major CYP450 enzymes in human hepatocytes.

In vitro studies indicate that MMAE is a substrate and not an inhibitor of the efflux transporter P‑glycoprotein (P-gp).

12.6 Immunogenicity

The observed incidence of anti-drug antibodies is highly dependent on the sensitivity and specificity of the assay. Differences in assay methods preclude meaningful comparisons of the incidence of anti-drug antibodies (ADA) in the studies described below with incidence of ADA in other studies, including those of ADCETRIS or of other brentuximab vedotin products.

Among adult patients with relapsed or refractory cHL and relapsed or refractory systemic ALCL in Studies 1 and 2 [see Clinical Studies (14.1) and (14.3)], treatment-emergent ADA (or anti-brentuximab vedotin antibodies) developed in 37% (58/156) of patients who were tested for anti-brentuximab vedotin antibodies. Approximately 7% of patients in these trials developed persistently positive antibodies (positive test at more than 2 time points) and 30% developed transiently positive antibodies (positive at 1 or 2 post-baseline time points). Two of the patients (1%) with persistently positive antibodies experienced adverse reactions consistent with infusion reactions that led to discontinuation of treatment. Overall, a higher incidence of infusion-related reactions was observed in patients who developed persistently positive antibodies. The incidence of treatment-emergent neutralizing antibodies against brentuximab vedotin was 62% (36/58). The effect of anti-brentuximab vedotin antibodies on efficacy is not known.

Among pediatric patients with previously untreated high risk cHL in Study 7 [see Clinical Studies (14.1)], of the 26 patients tested, none of the patients tested positive for anti-brentuximab vedotin antibodies.

Among adult patients with LBCL in Study 8 [see Clinical Studies (14.5)], treatment-emergent anti-brentuximab vedotin antibodies developed in 8% (8/97) of patients who were tested. The effect of anti-brentuximab vedotin antibodies on efficacy is not known.

13 NONCLINICAL TOXICOLOGY

13.1 Carcinogenesis, Mutagenesis, Impairment of Fertility

Carcinogenicity studies with brentuximab vedotin or the small molecule (MMAE) have not been conducted.

MMAE was genotoxic in the rat bone marrow micronucleus study through an aneugenic mechanism. This effect is consistent with the pharmacological effect of MMAE as a microtubule-disrupting agent. MMAE was not mutagenic in the bacterial reverse mutation assay (Ames test) or the L5178Y mouse lymphoma forward mutation assay.

Fertility studies with brentuximab vedotin or MMAE have not been conducted. However, results of repeat-dose toxicity studies indicate the potential for brentuximab vedotin to impair female and male reproductive function and fertility. In a 4-week repeat-dose toxicity study in rats with weekly dosing at 0.5, 5, or 10 mg/kg brentuximab vedotin, seminiferous tubule degeneration, Sertoli cell vacuolation, reduced spermatogenesis, and aspermia were observed. Effects in animals were seen mainly at 5 and 10 mg/kg of brentuximab vedotin. These doses are approximately 3 and 6-fold the human recommended dose of 1.8 mg/kg, respectively, based on body weight.

MMAE-containing ADCs have been associated with adverse ovarian effects when administered to sexually immature animals. Adverse effects included decrease in, or absence of, secondary and tertiary ovarian follicles after weekly administration to cynomolgus monkeys in studies of 4-week duration. These effects showed a trend towards recovery 6 weeks after the end of dosing; no changes were observed in primordial follicles.

14 CLINICAL STUDIES

14.1 Classical Hodgkin Lymphoma

Randomized Clinical Trial in Previously Untreated Stage III or IV Classical Hodgkin Lymphoma (Study 5: ECHELON-1, NCT01712490)

The efficacy of ADCETRIS in combination with chemotherapy for the treatment of patients with previously untreated Stage III or IV cHL was evaluated in a randomized, open-label, 2-arm, multicenter trial. Of the 1334 total patients, 664 patients were randomized to the ADCETRIS + doxorubicin [A], vinblastine [V] and dacarbazine [D] (ADCETRIS + AVD) arm and 670 patients were randomized to the A+ bleomycin [B] + V + D (ABVD) arm. Patients in both treatment arms were treated intravenously on Days 1 and 15 of each 28-day cycle for up to 6 cycles. Dosing in each treatment arm was administered according to the following:

- ADCETRIS + AVD arm: ADCETRIS 1.2 mg/kg over 30 minutes, doxorubicin 25 mg/m^2, vinblastine 6 mg/m^2, and dacarbazine 375 mg/m^2
- ABVD arm: doxorubicin 25 mg/m^2, bleomycin 10 units/m^2, vinblastine 6 mg/m^2, and dacarbazine 375 mg/m^2

Efficacy was established based on modified progression-free survival (modified PFS) per independent review facility (IRF). A modified PFS event is defined as progression, death, or receipt of additional anticancer therapy for patients who are not in a complete response (CR) after completion of frontline therapy.

Patients had Stage III (36%) or IV disease (64%), and 62% had extranodal involvement at diagnosis. Most patients were male (58%) and white (84%). The median age was 36 years (range, 18‑83); 186 patients (14%) were 60 years or older.

The efficacy results are summarized in Table 13 and Figure 1.

Table 13: Efficacy Results in Patients with Previously Untreated Stage III or IV Classical Hodgkin Lymphoma (Study 5: ECHELON‑1)
Modified Progression-Free Survival per IRF [At the time of analysis, the median follow-up time for both arms was 24.6 months.] | ADCETRIS + AVD N=664 | ABVD N=670
Number of events (%) | 117 (18%) | 146 (22%)
Median months (95% CI) | NE [Not estimable.] | NE
Hazard ratio (95% CI) [Hazard ratio (A+AVD/ABVD) and 95% confidence intervals are based on a stratified Cox’s proportional hazard regression model with stratification factors region and number of International Prognostic Factor Project (IPFP) risk factors at baseline with treatment as the explanatory variable in the model.] | 0.77 (0.60, 0.98)
P-value [P-value is from a stratified log-rank test with stratification factors baseline IPFP group and region; alpha = 0.05.] | 0.035
Reason leading to a modified PFS event
Progressive disease | 90 (14) | 102 (15)
Death due to any cause | 18 (3) | 22 (3)
Receipt of additional anticancer therapy for patients not in CR after frontline therapy | 9 (1) | 22 (3)

At the time of the modified PFS analysis, the prespecified interim OS analysis did not demonstrate a significant difference. The CR rate per IRF assessment at the end of the randomized regimen was 73% on the ADCETRIS + AVD arm and 70% on the ABVD arm.

A prespecified second interim analysis showed a statistically significant improvement in OS in the ADCETRIS + AVD arm (39 deaths) compared to the ABVD arm (64 deaths). With an estimated median follow-up of 6.1 years, the stratified hazard ratio was 0.59 (95% CI, 0.396; 0.879), with a 2-sided p-value of 0.009 (significance level, 0.0365). Median OS was not reached in either treatment arm (Figure 2).

Randomized Clinical Trial in Previously Untreated High Risk Classical Hodgkin Lymphoma (Study 7, AHOD1331, NCT02166463)

The efficacy of ADCETRIS in combination with chemotherapy for the treatment of pediatric patients (2 to <22 years of age) with previously untreated, high risk cHL was evaluated in a randomized, open-label, actively controlled trial. High risk was defined as Ann Arbor Stage IIB with bulk disease, Stage IIIB, Stage IVA, and Stage IVB. Of the 600 total patients randomized, 300 were randomized to ADCETRIS + Doxorubicin [A], Vincristine [V], Etoposide [E], Prednisone [P], Cyclophosphamide [C] (ADCETRIS + AVEPC) arm and 300 patients were randomized to A+ Bleomycin [B]+V+E+P+C (ABVE-PC) arm. Patients in each treatment arm received up to 5 cycles of the following:

- ADCETRIS + AVEPC arm: ADCETRIS 1.8 mg/kg over 30 minutes (day 1), doxorubicin 25 mg/m^2 (days 1 and 2), vincristine 1.4 mg/m^2 (day 8), etoposide 125 mg/m^2 (days 1-3), prednisone 20 mg/m^2 BID (days 1-7), cyclophosphamide 600 mg/m^2 (days 1 and 2)
- ABVE-PC arm: doxorubicin 25 mg/m^2 (days 1 and 2), bleomycin 5 units/m^2 (day1) and 10 units/m^2 (day 8), vincristine 1.4 mg/m^2 (days 1 and 8), etoposide 125 mg/m^2 (days 1-3), prednisone 20 mg/m^2 BID (days 1-7), cyclophosphamide 600 mg/m^2 (days 1 and 2)

The median age was 15 years (range: 3-21 years); 53% were male, 74% were White, 11% Black, and 3% Asian. Nine patients were <6 years, 81 patients were 6 to <12 years, 448 patients were 12 to <18 years, and 62 patients were ≥18 years. Of the 600 enrolled patients, 20% had disease stage of IIB with bulk disease, 19% had IIIB, 29% had IVA, and 31% had IVB.

Efficacy was established based on event-free-survival (EFS), defined as the time from randomization to the earliest of disease progression or relapse, second malignancy, or death due to any cause. Efficacy results are summarized in Table 14.

Table 14: Efficacy Results in Pediatric Patients with Previously Untreated High Risk Classical Hodgkin Lymphoma (Study 7: AHOD1331)
Event-Free Survival | ADCETRIS + AVEPC N = 300 | ABVE-PC N = 300
Number of Events (%) | 23 (8) | 52 (17)
Median (95% CI) | NR | NR
Hazard Ratio (95% CI) [Hazard ratio (BV-AVEPC/ABVE-PC) and 95% confidence intervals are based on a Cox proportional hazard regression model stratified by clinical characteristics (Stage IIB with bulk vs. Stage IIIB vs. Stage IVA vs. Stage IVB) as recorded at randomization.] | 0.41 (0.25, 0.67)
P-value (log-rank test) [Two-sided p-value from log-rank test stratified by clinical characteristic (disease stage).] | 0.0002
NR = Not reached.

Randomized Placebo-Controlled Clinical Trial in Classical Hodgkin Lymphoma Post-Auto-HSCT Consolidation (Study 3: AETHERA, NCT01100502)

The efficacy of ADCETRIS in patients with cHL at high risk of relapse or disease progression post-auto-HSCT was studied in a randomized, double-blind, placebo-controlled clinical trial. Three hundred twenty-nine (329) patients were randomized 1:1 to receive placebo or ADCETRIS 1.8 mg/kg intravenously over 30 minutes every 3 weeks for up to 16 cycles, beginning 30–45 days post-auto-HSCT. Patients in the placebo arm with progressive disease per investigator could receive ADCETRIS as part of a separate trial. The primary endpoint was progression-free survival (PFS) determined by independent review facility (IRF). Standard international guidelines were followed for infection prophylaxis for HSV, VZV, and PJP post-auto-HSCT [see Clinical Trial Experience (6.1)].

High risk of post-auto-HSCT relapse or progression was defined according to status following frontline therapy: refractory, relapse within 12 months, or relapse ≥12 months with extranodal disease. Patients were required to have obtained a complete response (CR), partial response (PR), or stable disease (SD) to most recent pre-auto-HSCT salvage therapy.

A total of 329 patients were enrolled and randomized (165 ADCETRIS, 164 placebo); 327 patients received study treatment. Patient demographics and baseline characteristics were generally balanced between treatment arms. The 329 patients ranged in age from 18–76 years (median, 32 years) and most were male (53%) and white (94%). Patients had received a median of 2 prior systemic therapies (range, 2–8) excluding autologous hematopoietic stem cell transplantation.

The efficacy results are summarized in Table 15. PFS is calculated from randomization to date of disease progression or death (due to any cause). The median PFS follow-up time from randomization was 22 months (range, 0–49). Study 3 (AETHERA) demonstrated a statistically significant improvement in IRF-assessed PFS and increase in median PFS in the ADCETRIS arm compared with the placebo arm. At the time of the PFS analysis, an interim overall survival analysis demonstrated no difference.

Table 15: Efficacy Results in Patients with Classical Hodgkin Lymphoma Post-Auto-HSCT Consolidation (Study 3: AETHERA)
Progression-Free Survival per IRF | ADCETRIS N = 165 | Placebo N = 164
Number of events (%) | 60 (36) | 75 (46)
Median months (95% CI) | 42.9 [Estimates are unreliable] (30.4, 42.9) | 24.1 (11.5, NE [Not estimable])
Stratified Hazard Ratio (95% CI) | 0.57 (0.40, 0.81)
Stratified Log-Rank Test P-value | 0.001

Clinical Trial in Relapsed Classical Hodgkin Lymphoma (Study 1, NCT00848926)

The efficacy of ADCETRIS in patients with cHL who relapsed after autologous hematopoietic stem cell transplantation was evaluated in one open-label, single-arm, multicenter trial. One hundred two (102) patients were treated with 1.8 mg/kg of ADCETRIS intravenously over 30 minutes every 3 weeks. An independent review facility (IRF) performed efficacy evaluations which included overall response rate (ORR = complete response [CR] + partial response [PR]) and duration of response as defined by clinical and radiographic measures including computed tomography (CT) and positron-emission tomography (PET) as defined in the 2007 Revised Response Criteria for Malignant Lymphoma (modified).

The 102 patients ranged in age from 15–77 years (median, 31 years) and most were female (53%) and white (87%). Patients had received a median of 5 prior therapies including autologous hematopoietic stem cell transplantation.

The efficacy results are summarized in Table 16. Duration of response is calculated from date of first response to date of progression or data cutoff date.

Table 16: Efficacy Results in Patients with Classical Hodgkin Lymphoma (Study 1)
 | N = 102
 | Percent (95% CI) | Duration of Response, in months
 | Percent (95% CI) | Median (95% CI) | Range
CR | 32 (23, 42) | 20.5 (12.0, NE [Not estimable]) | 1.4 to 21.9 [Follow-up was ongoing at the time of data submission]
PR | 40 (32, 49) | 3.5 (2.2, 4.1) | 1.3 to 18.7
ORR | 73 (65, 83) | 6.7 (4.0, 14.8) | 1.3 to 21.9

14.2 Systemic Anaplastic Large Cell Lymphoma and Other CD30-Expressing Peripheral T-Cell Lymphomas

Randomized Clinical Trial in Previously Untreated Systemic Anaplastic Large Cell Lymphoma or Other CD30-Expressing Peripheral T-Cell Lymphomas (Study 6: ECHELON-2, NCT01777152)

The efficacy of ADCETRIS in combination with chemotherapy for the treatment of adult patients with previously untreated, CD30-expressing PTCL was evaluated in a multicenter, randomized, double-blind, double-dummy, actively controlled trial. For enrollment, the trial required CD30 expression ≥10% per immunohistochemistry. The trial excluded patients with primary cutaneous CD30-positive T-cell lymphoproliferative disorders and lymphomas. The trial required hepatic transaminases ≤3 times ULN, total bilirubin ≤1.5 times ULN, and serum creatinine ≤2 times ULN.

Of the 452 total patients, 226 patients were randomized to the ADCETRIS + CHP arm and 226 patients were randomized to the CHOP arm. Patients in both treatment arms were treated intravenously on Day 1 of each 21-day cycle for 6 to 8 cycles; prednisone was administered orally on Days 1‑5. Dosing in each treatment arm was administered according to the following:

- ADCETRIS + CHP arm: ADCETRIS 1.8 mg/kg over 30 minutes, cyclophosphamide 750 mg/m^2, doxorubicin 50 mg/m^2, and prednisone 100 mg orally
- CHOP arm: cyclophosphamide 750 mg/m^2, doxorubicin 50 mg/m^2, vincristine 1.4 mg/m^2, and prednisone 100 mg orally

The median age was 58 years (range: 18 to 85), 63% were male, 62% were White, 22% were Asian, and 78% had an ECOG performance status of 0-1. Of the 452 patients enrolled, the disease subtypes included patients with systemic ALCL [70%; 48% anaplastic lymphoma kinase (ALK) negative and 22% ALK positive], PTCL NOS (16%), angioimmunoblastic T-cell lymphoma (12%), adult T-cell leukemia/lymphoma (2%), and enteropathy-associated T-cell lymphoma (<1%). Most patients had Stage III or IV disease (81%) and a baseline international prognostic index of 2 or 3 (63%).

During randomized treatment, on the ADCETRIS + CHP arm, 70% of patients received 6 cycles and 18% of patients received 8 cycles. On the CHOP arm, 62% of patients received 6 cycles and 19% received 8 cycles.

Efficacy was based on IRF-assessed PFS, which was defined as time from randomization to progression, death due to any cause, or receipt of subsequent anticancer chemotherapy to treat residual or progressive disease. Other efficacy endpoints included PFS in patients with systemic ALCL, overall survival, complete response rate, and overall response rate. Efficacy results are summarized in Table 17. Kaplan-Meier curves for PFS and overall survival are presented in Figure 5 and Figure 6, respectively.

Table 17: Efficacy Results in Patients with Previously Untreated, CD30-Expressing PTCL (Study 6: ECHELON‑2)
Outcomes per IRF [Efficacy endpoints were tested at a two-sided alpha level 0.05 in the following order: PFS in ITT, PFS in the sALCL subgroup, complete remission rate, overall survival, and objective response rate in ITT.] | ADCETRIS + CHP N=226 | CHOP N=226
PFS
Number of events, n (%) | 95 (42) | 124 (55)
Median PFS, months (95% CI) | 48.2 (35.2, NE) | 20.8 (12.7, 47.6)
Hazard ratio (95% CI) [Hazard ratio (A+CHP/CHOP) and 95% confidence intervals are based on a stratified Cox’s proportional hazard regression model with the following stratification factors (ALK-positive sALCL and International Prognostic Index [IPI] score at baseline).] | 0.71 (0.54, 0.93)
P-value [P-value is calculated using a stratified log-rank test.] | 0.011
Reason leading to a PFS event, n (%)
Progressive disease | 71 (31) | 86 (38)
Death | 13 (6) | 17 (8)
Receipt of subsequent anticancer chemotherapy to treat residual or progressive disease | 11 (5) | 21 (9)
PFS for patients with sALCL
N | 163 | 151
Number of patients with a PFS event, n (%) | 56 (34) | 73 (48)
Median PFS, months (95% CI) | 55.7 (48.2, NE) | 54.2 (13.4, NE)
Hazard ratio (95% CI) | 0.59 (0.42, 0.84)
P-value | 0.003
OS [Median OS follow-up in the ADCETRIS+CHP arm was 41.9 months; in the CHOP arm was 42.2 months.]
Number of deaths | 51 (23) | 73 (32)
Median OS, months (95% CI) | NE (NE, NE) | NE (54.2, NE)
Hazard ratio (95% CI) | 0.66 (0.46, 0.95)
P-value | 0.024
CR Rate [Best response per 2007 International Working Group Criteria at end of treatment.]
% (95% CI) | 68 (61, 74) | 56 (49, 62)
P-value [P-value is calculated using a stratified Cochran-Mantel-Haenszel test] | 0.007
ORR
% (95% CI) | 83 (78, 88) | 72 (66, 78)
P-value | 0.003
NE = Not estimable

14.3 Systemic Anaplastic Large Cell Lymphoma

Clinical Trial in Relapsed sALCL (Study 2, NCT00866047)

The efficacy of ADCETRIS in patients with relapsed sALCL was evaluated in one open-label, single-arm, multicenter trial. This trial included patients who had sALCL that was relapsed after prior therapy. Fifty-eight (58) patients were treated with 1.8 mg/kg of ADCETRIS administered intravenously over 30 minutes every 3 weeks. An IRF performed efficacy evaluations which included overall response rate (ORR = complete response [CR] + partial response [PR]) and duration of response as defined by clinical and radiographic measures including computed tomography (CT) and positron-emission tomography (PET) as defined in the 2007 Revised Response Criteria for Malignant Lymphoma (modified).

The 58 patients ranged in age from 14–76 years (median, 52 years) and most were male (57%) and white (83%). Patients had received a median of 2 prior therapies; 26% of patients had received prior autologous hematopoietic stem cell transplantation. Fifty percent (50%) of patients were relapsed, and 50% of patients were refractory to their most recent prior therapy. Seventy-two percent (72%) were anaplastic lymphoma kinase (ALK)-negative.

The efficacy results are summarized in Table 18. Duration of response is calculated from date of first response to date of progression or data cutoff date.

Table 18: Efficacy Results in Patients with Systemic Anaplastic Large Cell Lymphoma (Study 2)
 | N = 58
 | Percent (95% CI) | Duration of Response, in months
 | Percent (95% CI) | Median (95% CI) | Range
CR | 57 (44, 70) | 13.2 (10.8, NE [Not estimable]) | 0.7 to 15.9 [Follow-up was ongoing at the time of data submission]
PR | 29 (18, 41) | 2.1 (1.3, 5.7) | 0.1 to 15.8
ORR | 86 (77, 95) | 12.6 (5.7, NE) | 0.1 to 15.9

14.4 Primary Cutaneous Anaplastic Large Cell Lymphoma and CD30-Expressing Mycosis Fungoides

Randomized Clinical Trial in Primary Cutaneous Anaplastic Large Cell Lymphoma and CD30-expressing Mycosis Fungoides (Study 4: ALCANZA, NCT01578499)

The efficacy of ADCETRIS in patients with primary cutaneous anaplastic large cell lymphoma (pcALCL) or mycosis fungoides (MF) requiring systemic therapy was studied in ALCANZA, a randomized, open-label, multicenter clinical trial. In ALCANZA, one hundred thirty-one (131) patients were randomized 1:1 to receive ADCETRIS 1.8 mg/kg intravenously over 30 minutes every 3 weeks or physician’s choice of methotrexate (5 to 50 mg orally weekly) or bexarotene (300 mg/m^2 orally daily). The randomization was stratified by baseline disease diagnosis (MF or pcALCL). Patients could receive a maximum of 16 cycles (21-day cycle) of therapy every 3 weeks for those receiving brentuximab vedotin or 48 weeks of therapy for those in the control arm.

Patients with pcALCL must have received prior radiation or systemic therapy, and must have at least 1 biopsy with CD30-expression of ≥10%. Patients with MF must have received prior systemic therapy and have had skin biopsies from at least 2 separate lesions, with CD30-expression of ≥10% in at least 1 biopsy.

A total of 131 patients were randomized (66 ADCETRIS, 65 physician’s choice). The efficacy results were based on 128 patients (64 patients in each arm with CD30-expression of ≥10% in at least one biopsy). Among 128 patients, the patients’ age ranged from 22–83 years (median, 60 years), and 55% of them were male and 85% of them were white. Patients had received a median of 4 prior therapies (range, 0–15), including a median of 1 prior skin-directed therapy (range, 0–9) and 2 systemic therapies (range, 0–11). At study entry, patients were diagnosed as Stage 1 (25%), Stage 2 (38%), Stage 3 (5%), or Stage 4 (13%).

Efficacy was established based on the proportion of patients achieving an objective response (CR+PR) that lasts at least 4 months (ORR4). ORR4 was determined by independent review facility (IRF) using the global response score (GRS), consisting of skin evaluations per modified severity-weighted assessment tool (mSWAT), nodal and visceral radiographic assessment, and detection of circulating Sézary cells (MF patients only). Additional efficacy outcome measures included proportion of patients achieving a complete response (CR) per IRF, and progression-free survival (PFS) per IRF.

The efficacy results are summarized in Table 19 below and the Kaplan-Meier curves of IRF-assessed PFS are shown in Figure 7.

Table 19: Efficacy Results in Patients with Relapsed pcALCL or CD30-Expressing MF (Study 4: ALCANZA)
 | ADCETRIS N = 64 | Physician’s Choice [Physician’s choice of either methotrexate or bexarotene] N = 64
ORR4 [ORR4 is defined as proportion of patients achieving an objective response (CR+PR) that lasts at least 4 months]
Percent (95% CI [CI=Confidence Interval]) | 56.3 (44.1, 68.4) | 12.5 (4.4, 20.6)
P-value [Test of the treatment difference was stratified by baseline disease diagnosis (MF or pcALCL)] | <0.001
ORR | 67.2 (55.7, 78.7) | 20.3 (10.5, 30.2)
CR
Percent (95% CI) | 15.6 (7.8, 26.9) | 1.6 (0, 8.4)
P-value, [Adjusted for multiplicity] | 0.0066
PR | 51.6 (39.3, 63.8) | 18.8 (9.2, 28.3)
PFS
Number of events (%) | 36 (56.3) | 50 (78.1)
Median months (95% CI) | 16.7 (14.9, 22.8) | 3.5 (2.4, 4.6)
Hazard Ratio (95% CI) | 0.27 (0.17, 0.43)
Log-Rank Test P-value, | <0.001

Supportive trials include 2 single-arm trials, which enrolled patients with MF who were treated with ADCETRIS 1.8 mg/kg intravenously over 30 minutes every 3 weeks. Out of 73 patients with MF from the 2 pooled supportive trials, 34% (25/73) achieved ORR4. Among these 73 patients, 35 had 1% to 9% CD30-expression and 31% (11/35) achieved ORR4.

14.5 Relapsed or Refractory Large B-Cell Lymphoma (LBCL)

Randomized Clinical Trial in Relapsed or Refractory Large B-Cell Lymphoma (Study 8: ECHELON-3)

The efficacy of ADCETRIS in combination with lenalidomide and a rituximab product for the treatment of adult patients with relapsed or refractory LBCL after two or more lines of systemic therapy was evaluated in ECHELON-3 (NCT04404283), a randomized, multicenter, double-blind, placebo-controlled trial. Eligible patients were 18 years of age and older with relapsed or refractory LBCL, including DLBCL NOS, DLBCL arising from indolent lymphoma, or HGBL, an ECOG performance status of 0–2, and were not eligible to receive an auto-HSCT or CAR T-cell therapy. The study excluded patients with active CNS lymphoma or Grade 2 or higher peripheral neuropathy.

Patients were randomized 1:1 to receive ADCETRIS plus lenalidomide and a rituximab product or to receive placebo plus lenalidomide and a rituximab product until disease progression or unacceptable toxicity. Randomization was stratified by CD30 expression (≥1% versus <1%), prior allogenic or autologous HSCT therapy, prior CAR T-cell therapy and cell of origin (germinal-center B-cell like [GCB] or non-GCB). Dosing in each treatment arms as follows:

- ADCETRIS plus lenalidomide and rituximab arm: ADCETRIS 1.2 mg/kg via intravenous infusion every 3 weeks, lenalidomide 20 mg orally daily, and rituximab 375 mg/m^2 via intravenous infusion every 3 weeks. Starting with Cycle 2, rituximab intravenous treatment could be substituted with rituximab 1,400 mg and hyaluronidase human 23,400 Units via subcutaneous injection every 3 weeks.
- Placebo plus lenalidomide and rituximab arm: lenalidomide 20 mg orally daily, and rituximab 375 mg/m^2 via intravenous infusion every 3 weeks. Starting with Cycle 2, rituximab intravenous treatment could be substituted with rituximab 1,400 mg and hyaluronidase human 23,400 Units via subcutaneous injection every 3 weeks.

Prophylaxis with granulocyte-colony stimulating factor (G-CSF) was mandated for both arms.

Of the 230 patients randomized (112 to ADCETRIS plus lenalidomide and rituximab, 118 to placebo plus lenalidomide and rituximab), the median age was 71 years (range 21 to 89 years); 57% were male, 53% were White, 26% were Asian and 4% were Hispanic or Latino. Race and ethnicity was not reported in 46 (20%) patients. There were no Black or African American patients enrolled. Of the total 230 patients, 71% had DLBCL NOS, 26% had transformed disease from prior indolent lymphoma, 16% had HGBL with MYC and BCL2 and/or BCL6 rearrangements or HGBL NOS. Of the patients with DLBCL NOS, 73 (45%) and 91 (55%) had GCB and non-GCB subtypes, respectively. Twenty-nine percent of patients had received prior CAR T-cell therapy and 12% had received prior HSCT. The median number of prior systemic therapies was 3 (range 2-8) with 41% receiving 2 prior therapies and 50% receiving 3 or more prior therapies. Eighty four percent had refractory disease to last therapy.

The major efficacy outcome was overall survival (OS). Additional efficacy outcome measures included progression free survival (PFS) and Objective Response Rate (ORR) according to investigator assessment per the Lugano Criteria for Response Assessment 2014. The results are presented in Table 20 and Figures 8 and 9.

Table 20: Efficacy Results in Relapsed or Refractory LBCL (Study 8: ECHELON-3)
 | ADCETRIS + Lenalidomide + Rituximab; (N=112) | Placebo + Lenalidomide + Rituximab; (N=118)
Overall Survival
Deaths, n (%) | 58 (51.8) | 76 (64.4)
Median, months (95% CI) | 13.8 (10.3, 18.8) | 8.5 (5.4, 11.7)
HR (95% CI) [Hazard ratio and 95% CI based on a stratified Cox regression model.] | 0.63 (0.45, 0.89)
p-value [Two-sided p-value from a stratified log-rank test.] , [O’Brien Flemming efficacy boundary 2-sided p-value=0.0232.] | 0.0085
PFS per Investigator
Number (%) of patients with event | 71 (63.4) | 85 (72.0)
Progressive disease, n (%) | 56 (50.0) | 71 (60.2)
Death, n (%) | 15 (13.4) | 14 (11.9)
Median, months (95% CI) | 4.2 (2.9, 7.1) | 2.6 (1.4, 3.1)
HR (95% CI) | 0.53 (0.38, 0.73)
p-value | <0.0001
Objective Response Rate per Investigator
Objective response rate (CR or PR), n (%) | 72 (64.3) | 49 (41.5)
95% CI for ORR [Exact 95% CI computed using the Clopper-Pearson method (Clopper 1934).] | (54.7, 73.1) | (32.5, 51.0)
p-value [Two-sided p-value based on stratified Cochran-Mantel-Haenszel test (CMH).] | 0.0006
Complete response (CR), n (%) | 45 (40.2) | 22 (18.6)
CI = confidence interval; CR = complete response; HR = hazard ratio; PFS = progression free survival; OS = overall survival. Stratified analyses were based on the stratification factors of cell of origin (GCB, non-GCB) and CD30 status (≥1%, <1%) at randomization.

Figure 8: Kaplan-Meier Curve of Overall Survival (Study 8: ECHELON-3)

Figure 9: Kaplan-Meier Curve of Progression-Free Survival (Study 8: ECHELON-3)

15 REFERENCES

1. OSHA Hazardous Drugs. OSHA. [Accessed on 30 July 2013, from http://www.osha.gov/SLTC/hazardousdrugs/index.html]

16 HOW SUPPLIED/STORAGE AND HANDLING

How Supplied

ADCETRIS (brentuximab vedotin) for Injection is supplied as a sterile, white to off-white preservative-free lyophilized cake or powder in individually-boxed single-dose vials:

- NDC (51144-050-01), 50 mg brentuximab vedotin

Storage

Store vial refrigerated at 2°C to 8°C (36°F to 46°F) in the original carton to protect from light.

Special Handling

ADCETRIS is a hazardous product. Follow special handling and disposal procedures^1.

17 PATIENT COUNSELING INFORMATION

Peripheral Neuropathy

Advise patients that ADCETRIS can cause a peripheral neuropathy. They should be advised to report to their health care provider any numbness or tingling of the hands or feet or any muscle weakness [see Warnings and Precautions (5.1)].

Fever/Neutropenia

Advise patients to contact their health care provider if a fever of 100.5°F or greater or other evidence of potential infection such as chills, cough, or pain on urination develops [see Warnings and Precautions (5.3)].

Infusion Reactions

Advise patients to contact their health care provider if they experience signs and symptoms of infusion reactions including fever, chills, rash, or breathing problems within 24 hours of infusion [see Warnings and Precautions (5.2)].

Hepatotoxicity

Advise patients to report symptoms that may indicate liver injury, including fatigue, anorexia, right upper abdominal discomfort, dark urine, or jaundice [see Warnings and Precautions (5.8)].

Progressive Multifocal Leukoencephalopathy

Instruct patients receiving ADCETRIS to immediately report if they have any of the following neurological, cognitive, or behavioral signs and symptoms or if anyone close to them notices these signs and symptoms [see Boxed Warning, Warnings and Precautions (5.9)]:

- changes in mood or usual behavior
- confusion, thinking problems, loss of memory
- changes in vision, speech, or walking
- decreased strength or weakness on one side of the body

Pulmonary Toxicity

Instruct patients to report symptoms that may indicate pulmonary toxicity, including cough or shortness of breath [see Warnings and Precautions (5.10)].

Acute Pancreatitis

Advise patients to contact their health care provider if they develop severe abdominal pain [see Warnings and Precautions (5.12)].

Gastrointestinal Complications

Advise patients to contact their health care provider if they develop severe abdominal pain, chills, fever, nausea, vomiting, or diarrhea [see Warnings and Precautions (5.12)].

Hyperglycemia

Educate patients about the risk of hyperglycemia and how to recognize associated symptoms [see Warnings and Precautions (5.13)].

Females and Males of Reproductive Potential

ADCETRIS can cause fetal harm. Advise women receiving ADCETRIS to use effective contraception during ADCETRIS treatment and for 2 months after the last dose of ADCETRIS.

Advise males with female sexual partners of reproductive potential to use effective contraception during ADCETRIS treatment and for 4 months after the last dose of ADCETRIS [see Use in Specific Populations (8.3)].

Advise patients to report pregnancy immediately [see Warnings and Precautions (5.14)].

Lactation

Advise patients to avoid breastfeeding while receiving ADCETRIS [see Use in Specific Populations (8.2)].

Manufactured by:
Seagen Inc.
Bothell, WA 98021
1-855-473-2436
U.S. License 2257

ADCETRIS, Seagen and are US registered trademarks of Seagen Inc.
© 2025 Seagen Inc., Bothell, WA 98021. All rights reserved.
LAB-1598-1.0

PACKAGE LABEL

NDC 51144-050-01
ADCETRIS®
(brentuximab vedotin)
FOR INJECTION
50 mg/vial
Single-dose vial. Discard unused portion.
Reconstitution and dilution required
For intravenous use only
Rx Only
Recommended Storage:
Store vial at 2°C to 8°C (36°F to 46°F) in original carton
to protect from light.
See Prescribing Information for dosage and dilution.
Manufactured by Seagen Inc., Bothell, WA 98021
U.S. License No. 2257
Seagen®
123456
MMMYYYY

NDC 51144-050-01
ADCETRIS®
(brentuximab vedotin)
FOR INJECTION
50 mg/vial
Single-dose vial. Discard unused portion.
Reconstitution and dilution required
For intravenous use only
Seagen®
Rx Only
Each vial contains 50 mg of Brentuximab vedotin.
No Preservative.
After reconstitution with 10.5 mL of Sterile Water
for Injection, USP, the concentration of ADCETRIS
(brentuximab vedotin) is 5 mg/mL.
Recommended Dosage:
See Prescribing Information.
Manufactured by:
Seagen Inc.
Bothell, WA 98021
U.S. License No. 2257
For more information:
1-855-4SEAGEN
Recommended Storage:
Store vial at 2°C to 8°C (36°F to 46°F) in original carton to protect from light.
No U.S. Standard of Potency.
ADCETRIS, SEAGEN AND are US registered trademarks of Seagen Inc.
© 2021 Seagen Inc.
All rights reserved. Printed in USA.
LOT 123456
EXP MMMYYYY
SN 12345678901234
GTIN 12345678901234